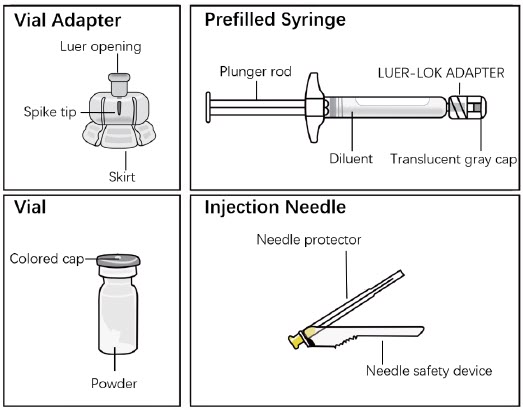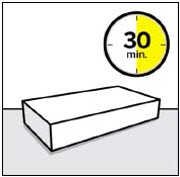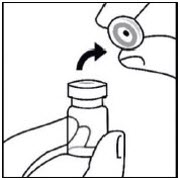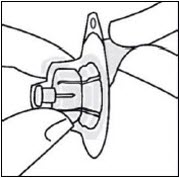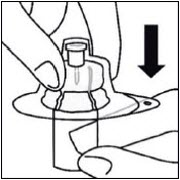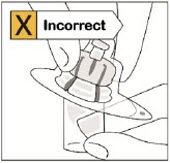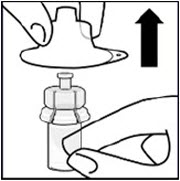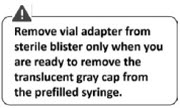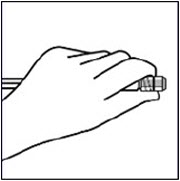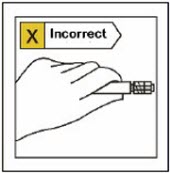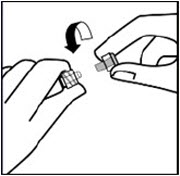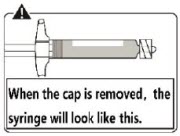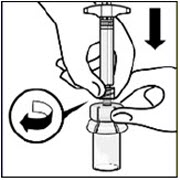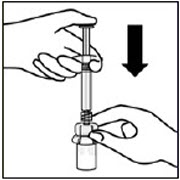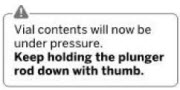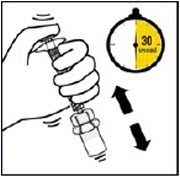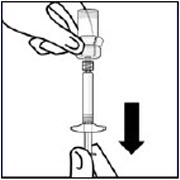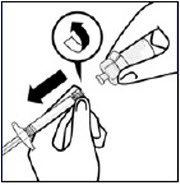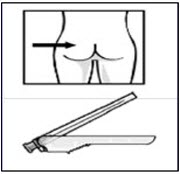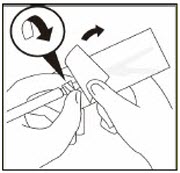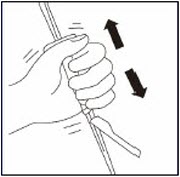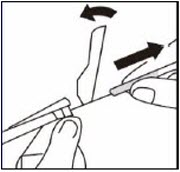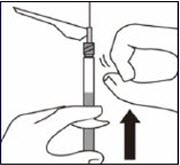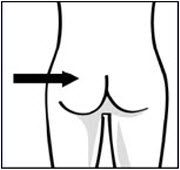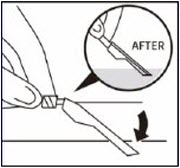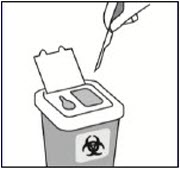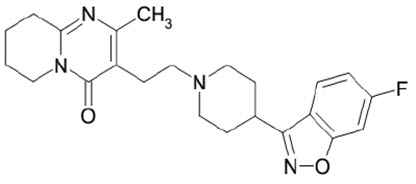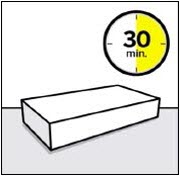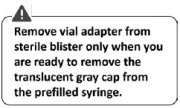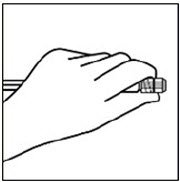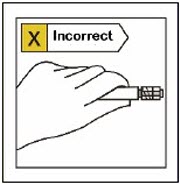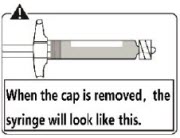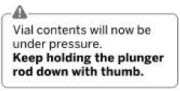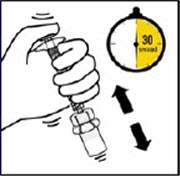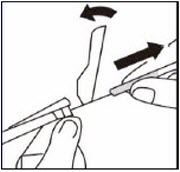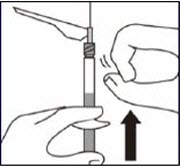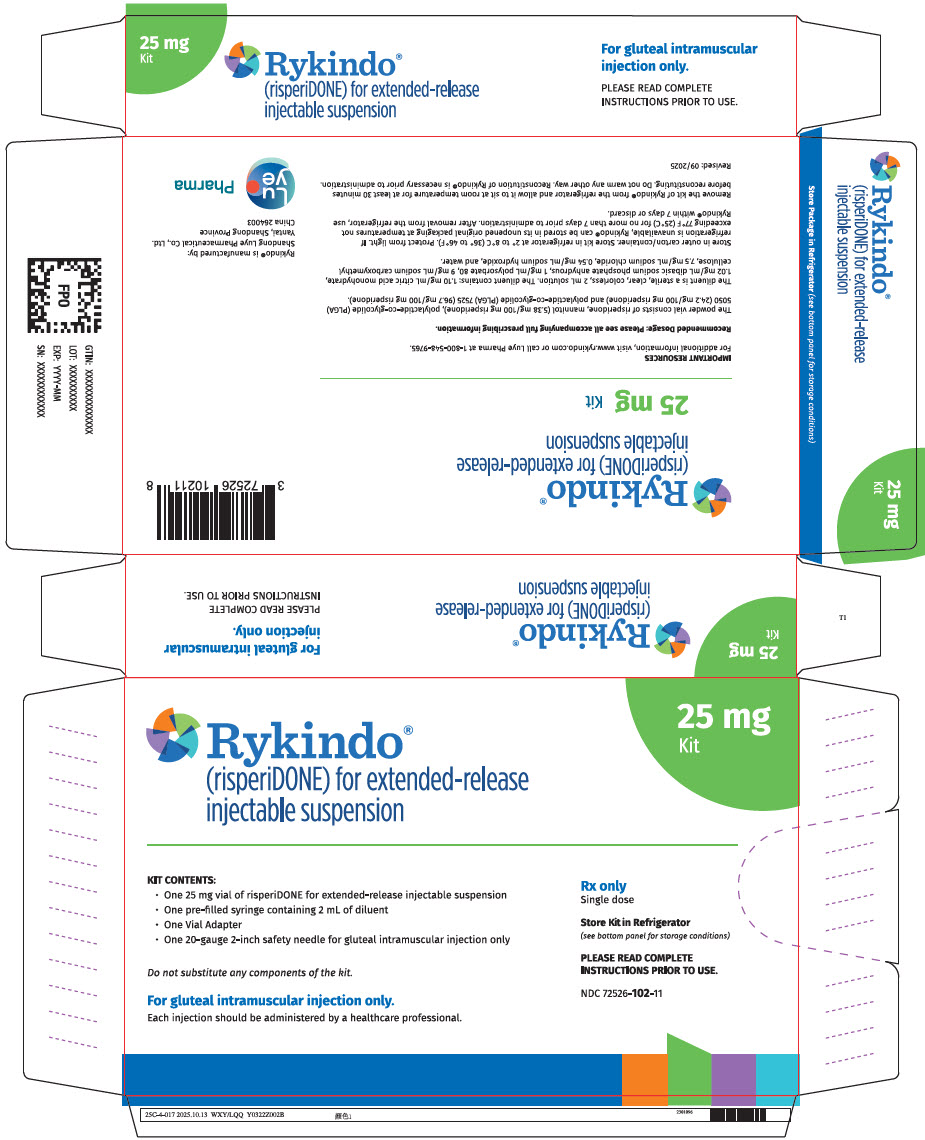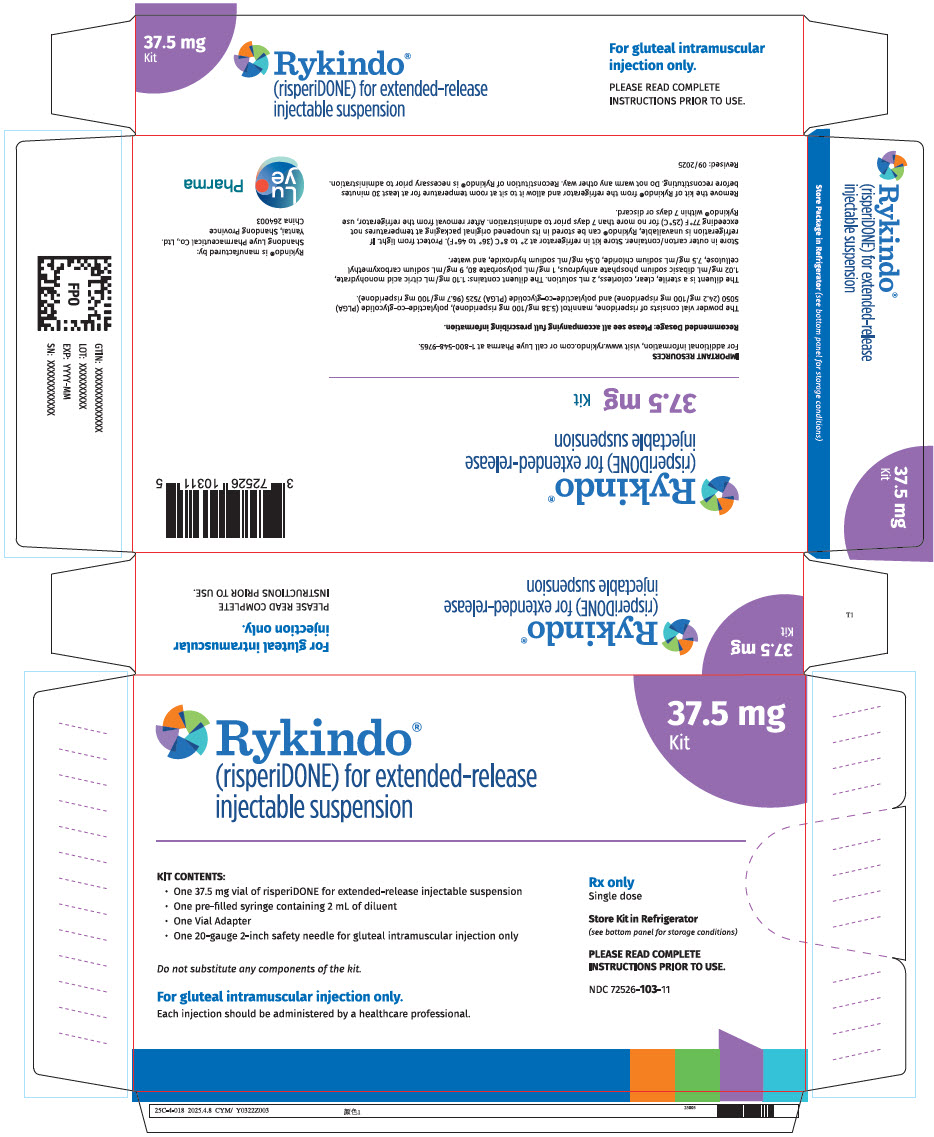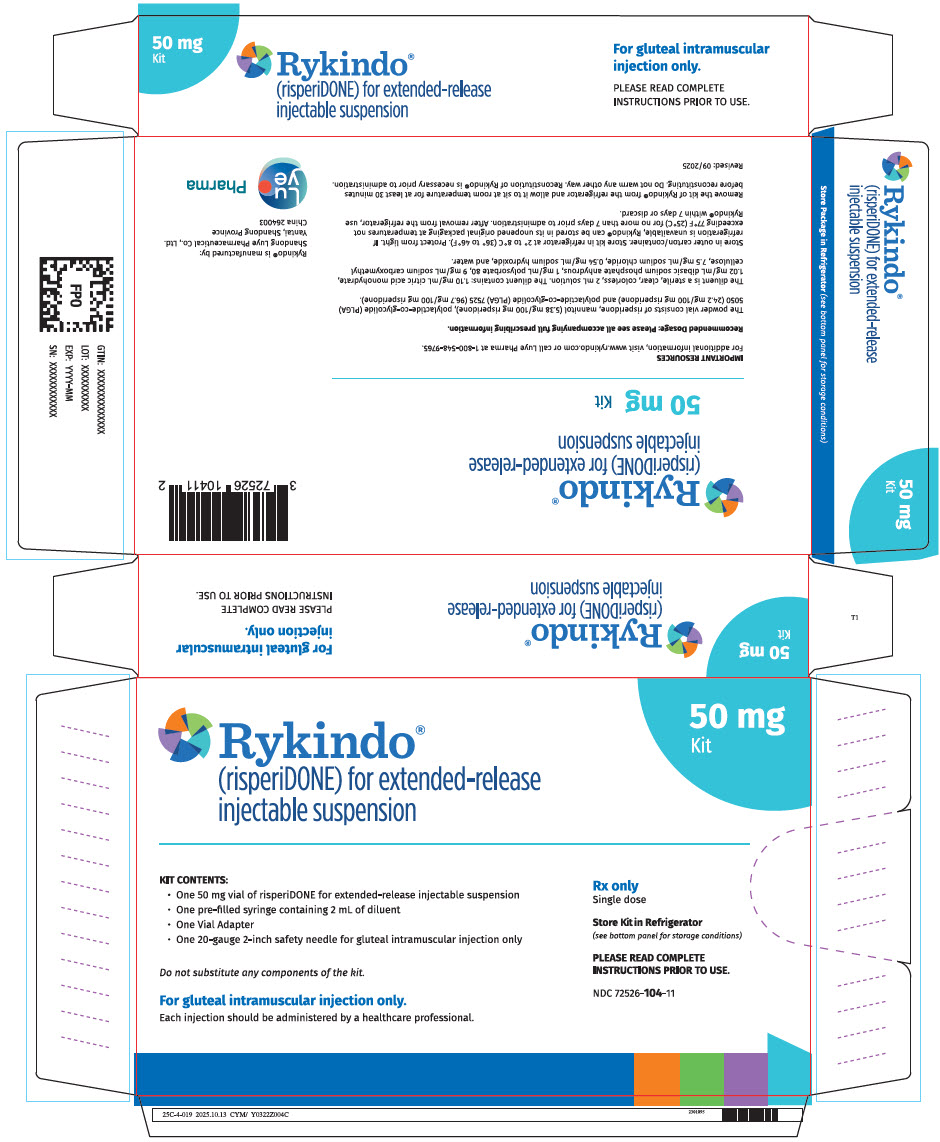 DRUG LABEL: Rykindo 
NDC: 72526-102 | Form: KIT | Route: INTRAMUSCULAR
Manufacturer: Shandong Luye Pharmaceutical Co., Ltd.
Category: prescription | Type: HUMAN PRESCRIPTION DRUG LABEL
Date: 20260205

ACTIVE INGREDIENTS: Risperidone 25 mg/2 mL
INACTIVE INGREDIENTS: DL-LACTIDE AND GLYCOLIDE (75:25) COPOLYMER 140000 ACID; DL-LACTIDE AND GLYCOLIDE (50:50) COPOLYMER 46000 ACID; MANNITOL; CITRIC ACID MONOHYDRATE; SODIUM PHOSPHATE, DIBASIC, ANHYDROUS; POLYSORBATE 80; CARBOXYMETHYLCELLULOSE SODIUM, UNSPECIFIED; SODIUM CHLORIDE; SODIUM HYDROXIDE; WATER

HIGHLIGHTS OF PRESCRIBING INFORMATION

These highlights do not include all the information needed to use RYKINDO® safely and effectively. See full prescribing information for RYKINDO®.
RYKINDO® (risperidone) for extended-release injectable suspension, for intramuscular use
Initial U.S. Approval: 1993

WARNING: INCREASED MORTALITY IN ELDERLY PATIENTS WITH DEMENTIA-RELATED PSYCHOSIS

See full prescribing information for complete boxed warning.

Elderly patients with dementia-related psychosis treated with antipsychotic drugs are at an increased risk of death. RYKINDO is not approved for use in patients with dementia-related psychosis. (5.1)

RECENT MAJOR CHANGES

Dosage and Administration (2.6, 2.7) | 1/2026

1 INDICATIONS AND USAGE

RYKINDO is an atypical antipsychotic indicated:

- for the treatment of schizophrenia in adults. (1)
- as monotherapy or as adjunctive therapy to lithium or valproate for the maintenance treatment of bipolar I disorder in adults. (1)

2 DOSAGE AND ADMINISTRATION

- Establish tolerability with oral risperidone prior to initiating treatment with RYKINDO. (2.1)
- Administer RYKINDO by intramuscular (IM) injection in the gluteal muscle by a healthcare provider. Do not administer by any other route. (2.1)
- Recommended dosage of RYKINDO is 25 mg intramuscular (IM) every 2 weeks. Patients not responding to 25 mg may benefit from 37.5 mg or 50 mg. Dosage titration should not be made more frequently than every 4 weeks. The maximum recommended dosage should not exceed 50 mg every 2 weeks. (2.2, 2.3)
- Administer the first dose of RYKINDO along with 7 days of oral risperidone. (2.2, 2.3)
- Renal or Hepatic Impairment: Titrate with oral risperidone up to at least 2 mg prior to initiating treatment with RYKINDO. (2.6)
- See Full Prescribing Information for important preparation and administration instructions. (2.8)

3 DOSAGE FORMS AND STRENGTHS

For extended-release injectable suspension: 25 mg, 37.5 mg, and 50 mg. (3)

4 CONTRAINDICATIONS

Known hypersensitivity to risperidone, paliperidone, or to any components in RYKINDO. (4)

5 WARNINGS AND PRECAUTIONS

- Cerebrovascular Adverse Reactions in Elderly Patients with Dementia-Related Psychosis: Increased risk of cerebrovascular adverse reactions (e.g., stroke, transient ischemia attack). (5.2)
- Neuroleptic Malignant Syndrome (NMS): Manage with immediate discontinuation and close monitoring. (5.3)
- Tardive Dyskinesia: Discontinue treatment if clinically appropriate. (5.4)
- Metabolic Changes: Monitor for hyperglycemia/diabetes mellitus, dyslipidemia, and weight gain. (5.5)
- Hyperprolactinemia: Prolactin elevations occur and persist during chronic administration. Long-standing hyperprolactinemia, when associated with hypogonadism, can lead to decreased bone density in males and females. (5.6)
- Orthostatic Hypotension and Syncope: Monitor heart rate and blood pressure and warn patients with known cardiovascular disease or cerebrovascular disease, and risk of dehydration or syncope. (5.7)
- Leukopenia, Neutropenia, and Agranulocytosis: Perform complete blood cell counts (CBC) in patients with a history of clinically significant low white blood cell count (WBC) or history of leukopenia or neutropenia. Consider discontinuing RYKINDO if clinically significant decline in WBC occurs in the absence of other causative factors. (5.9)
- Potential for Cognitive and Motor Impairment: Use caution when operating machinery. (5.10)
- Seizures: Use cautiously in patients with a history of seizures or with conditions that potentially lower the seizure threshold. (5.11)
- Priapism: Priapism has been reported during postmarketing use of other risperidone products. Severe priapism may require surgical intervention. (5.13)

6 ADVERSE REACTIONS

The most common adverse reactions in patients with schizophrenia (≥ 5%) were headache, parkinsonism, dizziness, akathisia, fatigue, constipation, dyspepsia, sedation, weight increase, pain in extremity, and dry mouth. (6)

The most common adverse reactions in patients with bipolar disorder were (5% in monotherapy trial) weight increased and (≥ 10% in adjunctive therapy trial) tremor and parkinsonism. (6)

To report SUSPECTED ADVERSE REACTIONS, contact Shandong Luye Pharmaceutical Co., Ltd. at 1-800-548-9765 or FDA at 1-800-FDA-1088 or www.fda.gov/medwatch.

7 DRUG INTERACTIONS

- Strong CYP2D6 inhibitors (e.g., fluoxetine, paroxetine): increase risperidone plasma concentration. (2.7, 7.1)
- Strong CYP3A4 inducers (e.g., carbamazepine): decrease plasma concentrations of risperidone. (2.7, 7.1)

8 USE IN SPECIFIC POPULATIONS

Pregnancy: May cause extrapyramidal and/or withdrawal symptoms in neonates with third trimester exposure. (8.1)

FULL PRESCRIBING INFORMATION

WARNING: INCREASED MORTALITY IN ELDERLY PATIENTS WITH DEMENTIA-RELATED PSYCHOSIS

Elderly patients with dementia-related psychosis treated with antipsychotic drugs are at an increased risk of death. RYKINDO is not approved for the treatment of patients with dementia-related psychosis [see Warnings and Precautions (5.1)].

1 INDICATIONS AND USAGE

RYKINDO is indicated:

- for the treatment of schizophrenia in adults
- as monotherapy or as adjunctive therapy to lithium or valproate for the maintenance treatment of bipolar I disorder in adults

2 DOSAGE AND ADMINISTRATION

2.1 General Administration Information

For patients who have never taken oral risperidone, establish tolerability with oral risperidone prior to initiating RYKINDO.

RYKINDO should be administered every 2 weeks by intramuscular (IM) gluteal injection. Each injection should be administered by a health care professional. Do not administer by any other route. Alternate injections between the two buttocks. Do not combine two different dose strengths of RYKINDO in a single administration.

For detailed preparation and administration instructions, see Dosage and Administration (2.8).

2.2 Dosage Recommendations for the Treatment of Schizophrenia

The recommended dosage of RYKINDO for the treatment of schizophrenia is 25 mg every 2 weeks. Administer the first dose of RYKINDO along with 7 days of oral risperidone.

Patients not responding to 25 mg may benefit from a higher dose of 37.5 mg or 50 mg. The maximum dose should not exceed 50 mg every 2 weeks. No additional benefit was observed with dosages greater than 50 mg of risperidone long-acting injection (intramuscular); however, a higher incidence of adverse reactions was observed. Dose titration should not be made more frequently than every 4 weeks.

2.3 Dosage Recommendations for Maintenance Treatment of Bipolar I Disorder

The recommended dosage of RYKINDO for monotherapy or adjunctive therapy to lithium or valproate for the maintenance treatment of bipolar I disorder is 25 mg every 2 weeks. Administer the first dose of RYKINDO along with 7 days of oral risperidone.

Some patients may benefit from a higher dose of 37.5 mg or 50 mg. Dosages above 50 mg have not been studied in this population. Dose titration should not be made more frequently than every 4 weeks.

2.4 Patients Currently Receiving Risperidone Long-acting Injection 2-week Intramuscular Formulation (e.g., Risperdal Consta)

The RYKINDO dose for patients receiving a risperidone long-acting injection (intramuscular) every two week formulation (e.g., Risperdal Consta) should be the same as that of the previous treatment. The first injection of RYKINDO should be given 4 weeks (no later than 5 weeks) after the last injection of the previous treatment. Supplementation with oral risperidone is not recommended [see Clinical Pharmacology (12.3)]. Titration should not be made more frequently than every 4 weeks.

2.5 Reinitiation of Treatment in Patients Previously Discontinued

There are no data to specifically address reinitiation of treatment. When restarting patients who have had an interval off treatment with RYKINDO, the previously established dosage should be reinitiated if there has been no change in the patient's general medical condition. Supplementation with oral risperidone is also required.

2.6 Dosage Recommendations for Patients with Renal or Hepatic Impairment

Patients with renal or hepatic impairment should be treated with titrated oral risperidone prior to initiating treatment with RYKINDO [see Use in Specific Populations (8.6, 8.7) and Clinical Pharmacology (12.3)]. The recommended starting dose is 0.5 mg oral risperidone twice daily during the first week, which can be increased to 1 mg twice daily or 2 mg once daily during the second week. If a total daily dose of at least 2 mg oral risperidone is well tolerated, RYKINDO 25 mg can be administered every 2 weeks with oral supplementation for 7 days following the first injection [see Dosing and Administration (2.2, 2.3)]. In some patients, slower titration may be appropriate.

2.7 Dosage Recommendations for Concomitant Use of RYKINDO with Strong CYP2D6 Inhibitors and Strong CYP3A4 Inducers

Co-administration of carbamazepine and other CYP3A4 enzyme inducers (e.g., phenytoin, rifampin, phenobarbital) with risperidone would be expected to cause decreases in the plasma concentrations of the sum of risperidone and 9-hydroxyrisperidone combined, which could lead to decreased efficacy of RYKINDO treatment. The risperidone dose needs to be titrated accordingly for patients receiving these enzyme inducers, especially during initiation or discontinuation of therapy with these inducers [see Drug Interactions (7.1)]. At the initiation of therapy with carbamazepine or other known CYP3A4 hepatic enzyme inducers, patients should be closely monitored during the first 1 to 2 months because the dose of RYKINDO may need to be adjusted. A dose increase, or additional oral risperidone, needs to be considered. On discontinuation of carbamazepine or other CYP3A4 hepatic enzyme inducers, the dosage of RYKINDO should be re-evaluated and, if necessary, decreased. Patients may be placed on a lower dose of RYKINDO between 2 to 4 weeks before the planned discontinuation of carbamazepine or other CYP3A4 inducers to adjust for the expected increase in plasma concentrations of risperidone plus 9-hydroxyrisperidone. For patients treated with the recommended dose of 25 mg RYKINDO and discontinuing from carbamazepine or other CYP3A4 enzyme inducers, it is recommended to continue treatment with the 25-mg dose unless clinical judgment necessitates either lowering the dose to 12.5 mg, in which case a different risperidone long-acting injection intramuscular formulation should be used, or interruption of RYKINDO treatment.

Fluoxetine and paroxetine, CYP2D6 inhibitors, have been shown to increase the plasma concentration of risperidone by 2.5 to 2.8-fold and 3 to 9-fold, respectively. Fluoxetine did not affect the plasma concentration of 9-hydroxyrisperidone. Paroxetine lowered the concentration of 9-hydroxyrisperidone by about 10%. The dose of risperidone needs to be titrated accordingly when co-administering fluoxetine or paroxetine. When either concomitant fluoxetine or paroxetine is initiated or discontinued, the physician should re-evaluate the dose of RYKINDO. When initiation of fluoxetine or paroxetine is considered, patients may be placed on a lower dose of RYKINDO between 2 to 4 weeks before the planned start of fluoxetine or paroxetine therapy to adjust for the expected increase in plasma concentrations of risperidone. When fluoxetine or paroxetine is initiated in patients receiving the recommended dose of 25 mg RYKINDO it is recommended to continue treatment with the 25 mg dose unless clinical judgment necessitates either lowering the dose to 12.5 mg, in which case a different risperidone long-acting injection intramuscular formulation should be used, or interruption of RYKINDO treatment. The effects of discontinuation of concomitant fluoxetine or paroxetine therapy on the pharmacokinetics of risperidone and 9-hydroxyrisperidone have not been studied [see Drug Interactions (7.1)].

2.8 Preparation and Administration Instructions

- Read the instructions for preparation and administration below and consider referring to the separate Healthcare Provider "Instructions for Use" for additional preparation and administration considerations.
- For gluteal intramuscular injection only. Do not inject by any other route. Alternate injections between the two buttocks.
- Allow package to come to room temperature for at least 30 minutes prior to preparation. Prepare medication when you are ready to administer the dose.
- The components in the single-dose kit are shown in Figure 1.

Figure 1. Single-dose Kit Components

Step 1. Take out kit and connect vial adapter to vial

Wait 30 minutes
Remove dose pack from the refrigerator and allow to sit at room temperature for at least 30 minutes before reconstituting.
Do not warm any other way.

Remove cap from vial
Flip off colored cap from vial.
Wipe top of the gray stopper with an alcohol swab. Allow to air dry.
Do not remove gray rubber stopper.

Prepare vial adapter
Hold sterile blister as shown. Peel back and remove paper backing.
Do not remove vial adapter from blister.
Do not touch spike tip at any time. This will result in contamination.

Connect vial adapter to vial
Place vial on a hard surface and hold by the base. Center vial adapter over the gray rubber stopper. Push vial adapter straight down onto vial top until it snaps securely into place.
Do not place vial adapter on at an angle or diluent may leak upon transfer to the vial.

Step 2. Connect prefilled syringe to vial adapter

Remove sterile blister
Keep vial vertical to prevent leakage. Hold base of vial and pull up on the sterile blister to remove.
Do not shake.
Do not touch exposed luer opening on vial adapter.
This will result in contamination.

Use proper grip
Hold by the LUER-LOK ADAPTER at the tip of the syringe.
Do not hold syringe by the glass barrel during assembly.

Remove cap
Holding the transparent LUER-LOK ADAPTER, unscrew the translucent gray cap
Do not snap or cut off the translucent gray cap
Do not touch syringe tip. This will result in contamination.
The unscrewed cap can be discarded.

Connect syringe to vial adapter
Hold vial adapter by skirt to keep stationary.
Hold syringe by the LUER-LOK ADAPTER then turn it to connect with the luer opening of the vial adapter
Do not hold the glass syringe barrel. This may cause the LUER-LOK ADAPTER to loosen or detach.
Attach the syringe to the vial adapter with a firm clockwise twisting motion until it feels snug.
Do not over-tighten. Over-tightening may cause the syringe tip to break.

Step 3. Reconstitute powder

Inject diluent
Inject entire amount of diluent from syringe into the vial.

Suspend Powder in diluent
Continuing to hold down the plunger rod, shake vigorously for at least 30 seconds, as shown.
Check the suspension. When properly mixed, the suspension appears uniform, thick and milky in color.
Immediately proceed to the next step so suspension does not settle.

Transfer suspension to syringe
Invert vial completely. Slowly pull plunger rod down to withdraw entire contents from the vial into the syringe.

Remove vial adapter
Hold LUER-LOK ADAPTER on the syringe and unscrew from vial adapter.
Tear section of the vial label at the perforation. Apply detached label to the syringe for identification purposes.
Discard both vial and vial adapter appropriately.

Step 4. Attach Needle

Take out needle
Take out needle for gluteal injection.

Attach needle
Peel blister pouch open part way and use to grasp the base of the needle, as shown.
Holding the LUER-LOK ADAPTER on the syringe, attach syringe to needle luer connection with a firm clockwise twisting motion until snug.
Do not touch needle luer opening. This will result in contamination.

Resuspend Powder
Fully remove the blister pouch.
Just before injection, shake syringe vigorously for 20 to 30 seconds until there is no deposition of powder, as some settling will have occurred.

Step 5. Inject RYKINDO

Remove transparent needle protector
Move the needle safety device back towards the syringe, as shown. Then hold the LUER-LOK ADAPTER on syringe and carefully pull the transparent needle protector straight off.
Do not twist transparent needle protector, as the luer connection may loosen.

Remove air bubbles
Hold syringe upright and tap gently to make any air bubbles rise to the top.
Slowly and carefully press plunger rod upward to remove air.

Inject
Immediately inject entire contents of syringe intramuscularly into the upper-outer quadrant of the gluteal muscle of the patient.

Secure needle in safety device
Using one hand, place needle safety device at a 45-degree angle on a hard, flat surface. Press down with a firm, quick motion until needle is fully engaged in safety device.

Properly dispose of syringes
Check to confirm needle safety device is fully engaged.
Discard in an approved sharps container.

3 DOSAGE FORMS AND STRENGTHS

RYKINDO (risperidone) for extended-release injectable suspension, for intramuscular use is available in strengths of 25 mg, 37.5 mg, and 50 mg.

Each strength is provided as a single-dose kit consisting of: a vial containing a white to almost white powder, a pre-filled syringe containing 2 mL of a colorless, clear diluent, a vial adapter, and a needle (20 gauge 2-inch needle with needle protection device).

4 CONTRAINDICATIONS

RYKINDO is contraindicated in patients with a known hypersensitivity to risperidone, its metabolite, paliperidone, or to any of its components. Hypersensitivity reactions, including anaphylactic reactions and angioedema, have been reported in patients treated with risperidone or paliperidone.

5 WARNINGS AND PRECAUTIONS

5.1 Increased Mortality in Elderly Patients with Dementia-Related Psychosis

Elderly patients with dementia-related psychosis treated with antipsychotic drugs are at an increased risk of death. Analyses of 17 placebo-controlled trials (modal duration of 10 weeks), largely in patients taking atypical antipsychotic drugs, revealed a risk of death in drug-treated patients that was 1.6 to 1.7 times the risk of death in placebo-treated patients. Over the course of a typical 10-week controlled trial, the rate of death in drug-treated patients was about 4.5% versus about 2.6% in the placebo group. Although the causes of death were varied, most of the deaths appeared to be either cardiovascular (e.g., heart failure, sudden death) or infectious (e.g., pneumonia) in nature. Observational studies suggest that, similar to atypical antipsychotic drugs, treatment with conventional antipsychotic drugs may increase mortality. The extent to which the findings of increased mortality in observational studies may be attributed to the antipsychotic drug as opposed to some characteristic(s) of the patients is not clear.

RYKINDO is not approved for the treatment of dementia-related psychosis [see Boxed Warning and Warnings and Precautions (5.2)].

5.2 Cerebrovascular Adverse Reactions, Including Stroke, in Elderly Patients with Dementia-Related Psychosis

Cerebrovascular adverse reactions (e.g., stroke, transient ischemic attack), including fatalities, were reported in patients (mean age 85 years; range 73 to 97) in trials of oral risperidone in elderly patients with dementia-related psychosis. In placebo-controlled trials, there was a significantly higher incidence of cerebrovascular adverse reactions in patients treated with oral risperidone compared to patients treated with placebo. RYKINDO is not approved for the treatment of patients with dementia-related psychosis [see Warnings and Precautions (5.1)].

5.3 Neuroleptic Malignant Syndrome (NMS)

NMS, a potentially fatal symptom complex, has been reported in association with antipsychotic drugs. Clinical manifestations of NMS are hyperpyrexia, muscle rigidity, altered mental status including delirium, and autonomic instability (irregular pulse or blood pressure, tachycardia, diaphoresis, and cardiac dysrhythmia). Additional signs may include elevated creatine phosphokinase, myoglobinuria (rhabdomyolysis), and acute renal failure.

If NMS is suspected, immediately discontinue RYKINDO and provide symptomatic treatment and monitoring.

5.4 Tardive Dyskinesia

Tardive dyskinesia, a syndrome consisting of potentially irreversible, involuntary, dyskinetic movements, may develop in patients treated with antipsychotic drugs. Although the prevalence of the syndrome appears to be highest among the elderly, especially elderly women, it is impossible to predict which patients will develop the syndrome. Whether antipsychotic drug products differ in their potential to cause tardive dyskinesia is unknown.

The risk of developing tardive dyskinesia and the likelihood that it will become irreversible increase with the duration of treatment and the cumulative dose. The syndrome can develop after relatively brief treatment periods, even at low doses. It may also occur after discontinuation of treatment.

Tardive dyskinesia may remit, partially or completely, if antipsychotic treatment is discontinued. Antipsychotic treatment, itself, however, may suppress (or partially suppress) the signs and symptoms of the syndrome, possibly masking the underlying process. The effect that symptomatic suppression has upon the long-term course of the syndrome is unknown.

Given these considerations, RYKINDO should be prescribed in a manner that is most likely to minimize the occurrence of tardive dyskinesia. Chronic antipsychotic treatment should generally be reserved for patients: (1) who suffer from a chronic illness that is known to respond to antipsychotic drugs, and (2) for whom alternative, equally effective, but potentially less harmful treatments are not available or appropriate. In patients who do require chronic treatment, the lowest dose and the shortest duration of treatment producing a satisfactory clinical response should be used. Periodically reassess the need for continued treatment.

If signs and symptoms of tardive dyskinesia appear in a patient treated with RYKINDO, drug discontinuation should be considered. However, some patients may require treatment with RYKINDO despite the presence of the syndrome.

5.5 Metabolic Changes

Atypical antipsychotic drugs have caused metabolic changes, including hyperglycemia, diabetes mellitus, dyslipidemia, and body weight gain. While all of the drugs in the class have been shown to produce some metabolic changes, each drug has its own specific risk profile.

Hyperglycemia and Diabetes Mellitus

Hyperglycemia and diabetes mellitus, sometimes extreme and associated with ketoacidosis or hyperosmolar coma or death, have been reported in patients treated with atypical antipsychotics including risperidone. Assessment of the relationship between atypical antipsychotic use and glucose abnormalities is complicated by the possibility of an increased background risk of diabetes mellitus in patients with schizophrenia and the increasing incidence of diabetes mellitus in the general population. Given these confounders, the relationship between atypical antipsychotic use and hyperglycemia-related adverse events is not completely understood. However, epidemiological studies suggest an increased risk of hyperglycemia-related events in patients treated with the atypical antipsychotics. Precise risk estimates for hyperglycemia-related events in patients treated with atypical antipsychotics are not available.

Patients with an established diagnosis of diabetes mellitus who are started on atypical antipsychotics, including RYKINDO, should be monitored regularly for worsening glucose control. Patients with risk factors for diabetes mellitus (e.g., obesity, family history of diabetes) who are starting treatment with atypical antipsychotics, including RYKINDO, should undergo fasting blood glucose testing at the beginning of treatment and periodically during treatment. Any patient treated with atypical antipsychotics, including RYKINDO, should be monitored for symptoms of hyperglycemia including polydipsia, polyuria, polyphagia, and weakness. Patients who develop symptoms of hyperglycemia during treatment with atypical antipsychotics, including RYKINDO, should undergo fasting blood glucose testing. In some cases, hyperglycemia resolved when the atypical antipsychotic, including risperidone, was discontinued; however, some patients required continuation of anti-diabetic treatment despite discontinuation of risperidone.

Pooled data from 3 double-blind, placebo-controlled studies in patients with schizophrenia and 4 double-blind, placebo-controlled monotherapy studies in patients with bipolar mania with oral risperidone are presented in Table 1.

Table 1. Change in Random Glucose from Seven Placebo-Controlled, 3- to 8-Week, Fixed- or Flexible-Dose Studies in Adult Patients with Schizophrenia or Bipolar Mania with Oral Risperidone
 | Placebo | Oral Risperidone
 | Placebo | 1–8 mg/day | >8–16 mg/day
 | Mean change from baseline (mg/dL)
 | N=555 | N=748 | N=164
Serum Glucose | -1.4 | 0.8 | 0.6
 | Proportion of patients with shifts
Serum Glucose (<140 mg/dL to ≥200 mg/dL) | 0.6% (3/525) | 0.4% (3/702) | 0% (0/158)

In longer-term, controlled and uncontrolled studies in adult patients, oral risperidone was associated with a mean change in glucose of +2.8 mg/dL at Week 24 (N=151) and +4.1 mg/dL at Week 48 (N=50).

Dyslipidemia

Undesirable alterations in lipids have been observed in patients treated with atypical antipsychotics. Before or soon after initiation of antipsychotic medications, obtain a fasting lipid profile at baseline and monitor periodically during treatment.

Pooled data from 7 placebo-controlled, 3- to 8- week, fixed- or flexible-dose studies in adult patients with schizophrenia or bipolar mania are presented in Table 2.

Table 2. Change in Random Lipids from Seven Placebo-Controlled, 3- to 8-Week, Fixed- or Flexible-Dose Studies in Adult Patients with Schizophrenia or Bipolar Mania with Oral Risperidone
 | Placebo | Oral Risperidone
 | Placebo | 1–8 mg/day | >8–16 mg/day
 | Mean Change from Baseline (mg/dL)
 | N=559 | N=742 | N=156
Cholesterol
Change from baseline
 | 0.6 | 6.9 | 1.8
 | N=183 | N=307 | N=123
Triglycerides
Change from baseline
 | -17.4 | -4.9 | -8.3
 | Proportion of Patients with Shifts
Cholesterol | 2.7% | 4.3% | 6.3%
(<200 mg/dL to ≥240 mg/dL) | (10/368) | (22/516) | (6/96)
Triglycerides | 1.1% | 2.7% | 2.5%
(<500 mg/dL to ≥500 mg/dL) | (2/180) | (8/301) | (3/121)

In longer-term, controlled and uncontrolled studies, oral risperidone was associated with a mean change in (a) non-fasting cholesterol of +4.4 mg/dL at Week 24 (N=231) and +5.5 mg/dL at Week 48 (N=86); and (b) non-fasting triglycerides of +19.9 mg/dL at Week 24 (N=52).

Weight Gain

Weight gain has been observed with atypical antipsychotic use. Clinical monitoring of weight is recommended. Monitor weight at baseline and frequently thereafter.

Data from a placebo-controlled, 12-week, fixed-dose study in adult patients with schizophrenia are presented in Table 3.

Table 3. Mean Change in Body Weight (kg) and the Proportion of Patients with ≥7% Gain in Body Weight from a Placebo-Controlled, 12-Week, Fixed-Dose Study in Adult Patients with Schizophrenia
 | Placebo (N=83) | Risperidone Long-acting Injection (intramuscular)
 | Placebo (N=83) | 25 mg (N=90) | 50 mg (N=87)
Weight (kg) Change from baseline | -1.4 | 0.5 | 1.2
Weight Gain ≥7% increase from baseline | 6% | 10% | 8%

In an uncontrolled, longer-term, open-label study, risperidone long-acting injection (intramuscular) was associated with a mean change in weight of +2.1 kg at Week 24 (N=268) and +2.8 kg at Week 50 (N=199).

5.6 Hyperprolactinemia

As with other dopamine D2 receptor antagonists, risperidone elevates prolactin levels and the elevation persists during chronic administration. Risperidone is associated with higher levels of prolactin elevation than other antipsychotic agents.

Hyperprolactinemia may suppress hypothalamic gonadotropin-releasing hormone (GnRH), resulting in reduced pituitary gonadotropin secretion. This, in turn, may inhibit reproductive function by impairing gonadal steroidogenesis in both female and male patients [see Use in Specific Populations (8.3)]. Galactorrhea, amenorrhea, gynecomastia, and impotence have been reported in patients receiving prolactin-elevating compounds. Long-standing hyperprolactinemia when associated with hypogonadism may lead to decreased bone density in both female and male patients.

Tissue culture experiments indicate that approximately one-third of human breast cancers are prolactin dependent in vitro, a factor of potential importance if the prescription of these drugs is contemplated in a patient with previously detected breast cancer. An increase in pituitary gland, mammary gland, and pancreatic islet cell neoplasia (mammary adenocarcinomas, pituitary and pancreatic adenomas) was observed in the risperidone carcinogenicity studies conducted in mice and rats [see Nonclinical Toxicology (13.1)]. Published epidemiologic studies have shown inconsistent results when exploring the potential association between hyperprolactinemia and breast cancer.

5.7 Orthostatic Hypotension and Syncope

RYKINDO may induce orthostatic hypotension associated with dizziness, tachycardia, and in some patients, syncope, especially during the initial dose-titration period, probably reflecting its alpha-adrenergic antagonistic properties. Syncope was reported in 0.8% (12/1499 patients) of patients treated with risperidone long-acting injection (intramuscular) in multiple-dose studies. Patients should be instructed in nonpharmacologic interventions that help to reduce the occurrence of orthostatic hypotension (e.g., sitting on the edge of the bed for several minutes before attempting to stand in the morning and slowly rising from a seated position).

RYKINDO should be used with particular caution in (1) patients with known cardiovascular disease (history of myocardial infarction or ischemia, heart failure, or conduction abnormalities), cerebrovascular disease, and conditions which would predispose patients to hypotension, e.g., dehydration and hypovolemia, and (2) in the elderly and patients with renal or hepatic impairment. Monitoring of orthostatic vital signs should be considered in all such patients, and a dose reduction should be considered if hypotension occurs. Clinically significant hypotension has been observed with concomitant use of oral risperidone and antihypertensive medication.

5.8 Falls

Somnolence, postural hypotension, motor and sensory instability have been reported with the use of antipsychotics, including RYKINDO, which may lead to falls and, consequently, fractures or other fall-related injuries. For patients, particularly the elderly, with diseases, conditions, or medications that could exacerbate these effects, assess the risk of falls when initiating antipsychotic treatment and recurrently for patients on long-term antipsychotic therapy.

5.9 Leukopenia, Neutropenia, and Agranulocytosis

In clinical trial and/or postmarketing experience, leukopenia/neutropenia have been reported in temporal association with antipsychotic agents, including risperidone. Agranulocytosis has also been reported.

Possible risk factors for leukopenia/neutropenia include pre-existing low white blood cell count (WBC) and a history of drug-induced leukopenia/neutropenia. Patients with a history of a clinically significant low WBC or past drug-induced leukopenia/neutropenia should have their complete blood count (CBC) monitored frequently during the first few months of therapy. Discontinuation of RYKINDO should be considered at the first sign of a clinically significant decline in WBC in the absence of other causative factors.

Monitor patients with clinically significant neutropenia for fever or other symptoms or signs of infection and treat promptly if such symptoms or signs occur. Discontinue RYKINDO in patients with absolute neutrophil count <1000/mm^3 and follow their WBC until recovery.

5.10 Potential for Cognitive and Motor Impairment

RYKINDO, like other antipsychotics, may cause somnolence and has the potential to impair judgement, thinking, and motor skills. Somnolence was reported by 5% of patients treated with risperidone long-acting injection (intramuscular) in multiple-dose trials.

Patients should be cautioned about operating hazardous machinery, including motor vehicles, until they are reasonably certain that treatment with RYKINDO does not affect them adversely.

5.11 Seizures

During premarketing studies, seizure occurred in 0.3% of patients (5 out of 1, 499 patients) treated with risperidone long-acting injection (intramuscular). Use RYKINDO with caution in patients with a history of seizures or with conditions that lower the seizure threshold. Conditions that lower the seizure threshold may be more prevalent in older patients.

5.12 Dysphagia

Esophageal dysmotility and aspiration have been associated with antipsychotic drug use. Aspiration pneumonia is a common cause of morbidity and mortality in patients with advanced Alzheimer's dementia. Antipsychotic drugs, including RYKINDO should be used cautiously in patients at risk for aspiration [see Warnings and Precautions (5.1)].

5.13 Priapism

Priapism has been reported during postmarketing surveillance of other risperidone products. Severe priapism may require surgical intervention.

5.14 Body Temperature Dysregulation

Atypical antipsychotics may disrupt the body's ability to reduce core body temperature. Both hyperthermia and hypothermia have been reported in association with the use of oral risperidone or risperidone long-acting injection (intramuscular). Strenuous exercise, exposure to extreme heat, dehydration, and anticholinergic medications may contribute to an elevation in core body temperature; use RYKINDO with caution in patients who may experience these conditions.

5.15 Osteodystrophy and Tumors in Animals

Risperidone long-acting injection (intramuscular) produced osteodystrophy in male and female rats in a 1-year toxicity study and a 2-year carcinogenicity study at a dose of 40 mg/kg administered IM every 2 weeks.

Risperidone long-acting injection (intramuscular) produced renal tubular tumors (adenoma, adenocarcinoma) and adrenomedullary pheochromocytomas in male rats in the 2-year carcinogenicity study at 40 mg/kg administered IM every 2 weeks. In addition, risperidone long-acting injection (intramuscular) produced an increase in a marker of cellular proliferation in renal tissue in males in the 1-year toxicity study and in renal tumor-bearing males in the 2-year carcinogenicity study at 40 mg/kg administered IM every 2 weeks. Cellular proliferation was not measured at the low dose or in females in either study.

The effect dose for osteodystrophy and the tumor findings is 8 times the IM maximum recommended human dose (MRHD) (50 mg) on a mg/m^2 basis and is associated with a plasma exposure (AUC) twice the expected plasma exposure (AUC) at the IM MRHD. The no-effect dose for these findings was 5 mg/kg (equal to the IM MRHD on a mg/m^2 basis). Plasma exposure (AUC) at the no-effect dose was 33% of the expected plasma exposure (AUC) at the IM MRHD.

Neither the renal or adrenal tumors, nor osteodystrophy, were seen in studies of orally administered risperidone. Osteodystrophy was not observed in dogs at doses up to 14 times (based on AUC) the IM MRHD in a 1-year toxicity study.

The renal tubular and adrenomedullary tumors in male rats and other tumor findings are described in more detail in Section 13.1 (Carcinogenicity, Mutagenesis, Impairment of Fertility).

The relevance of these findings to humans is unknown.

6 ADVERSE REACTIONS

The following are discussed in more detail in other sections of the labeling:

- Increased mortality in elderly patients with dementia-related psychosis [see Boxed Warning and Warnings and Precautions (5.1)]
- Cerebrovascular adverse reactions, including stroke, in elderly patients with dementia-related psychosis [see Warnings and Precautions (5.2)]
- Neuroleptic malignant syndrome (NMS) [see Warnings and Precautions (5.3)]
- Tardive dyskinesia [see Warnings and Precautions (5.4)]
- Metabolic changes [see Warnings and Precautions (5.5)]
- Hyperprolactinemia [see Warnings and Precautions (5.6)]
- Orthostatic hypotension and syncope [see Warnings and Precautions (5.7)]
- Falls [see Warnings and Precautions (5.8)]
- Leukopenia, Neutropenia, and Agranulocytosis [see Warnings and Precautions (5.9)]
- Potential for cognitive and motor impairment [see Warnings and Precautions (5.10)]
- Seizures [see Warnings and Precautions (5.11)]
- Dysphagia [see Warnings and Precautions (5.12)]
- Priapism [see Warnings and Precautions (5.13)]
- Body temperature dysregulation [see Warnings and Precautions (5.14)]
- Osteodystrophy and tumors in animals [see Warnings and Precautions (5.15)]

6.1 Clinical Trials Experience

Because clinical trials are conducted under widely varying conditions, adverse reaction rates observed in the clinical trials of a drug cannot be directly compared to rates in the clinical trials of another drug and may not reflect the rates observed in clinical practice.

The safety of RYKINDO for the treatment of schizophrenia in adults and as monotherapy or as adjunctive therapy to lithium or valproate for the maintenance treatment of Bipolar I Disorder in adults is based on adequate and well-controlled studies of risperidone long-acting injection (intramuscular).

The data described in this section are derived from a clinical trial database consisting of 2,392 patients exposed to one or more doses of risperidone long-acting injection (intramuscular) for the treatment of schizophrenia. Of these 2,392 patients, 332 patients received risperidone long-acting injection (intramuscular) while participating in a 12-week double-blind, placebo-controlled trial. Two hundred two (202) of the 332 were patients with schizophrenia who received 25 mg or 50 mg risperidone long-acting injection (intramuscular). The conditions and duration of treatment with risperidone long-acting injection (intramuscular) in the other clinical trials varied greatly and included (in overlapping categories) double-blind, fixed- and flexible dose, placebo- or active-controlled studies and open-label phases of studies, inpatients and outpatients, and short-term (up to 12 weeks) and longer-term (up to 4 years) exposures.

In addition to the studies in patients with schizophrenia, safety data are presented from a trial assessing the efficacy and safety of risperidone long-acting injection (intramuscular) when administered as monotherapy for maintenance treatment in patients with bipolar I disorder.

Safety data are also presented from a trial assessing the efficacy and safety of risperidone long-acting injection (intramuscular) administered as adjunctive maintenance treatment in patients with bipolar disorder (intramuscular).

The most common adverse reactions in clinical trials of risperidone long-acting injection (intramuscular) in patients with schizophrenia (≥ 5%) were headache, parkinsonism, dizziness, akathisia, fatigue, constipation, dyspepsia, sedation, weight increased, pain in extremity, and dry mouth.

The most common adverse reactions in the double-blind, placebo-controlled periods of the bipolar disorder trials of risperidone long-acting injection (intramuscular) were weight increased (5% in the monotherapy trial) and tremor and parkinsonism (≥ 10% in the adjunctive treatment trial).

Table 4 lists the adverse reactions reported in 2% or more of risperidone long-acting injection-treated patients with schizophrenia in one 12-week double-blind, placebo-controlled trial.

Table 4. Adverse Reactions Occurring in ≥2% of Risperidone Long-acting Injection (intramuscular)-Treated Patients (Adults) with Schizophrenia in a 12-Week Double-Blind, Placebo-Controlled Trial
 | Risperidone Long-acting Injection (intramuscular) |  | Placebo
System/Organ Class Adverse Reaction | 25 mg % | 50 mg % | %
System/Organ Class Adverse Reaction | (N=99) | (N=103) | (N=98)
Eye disorders
Vision blurred | 2 | 3 | 0
Gastrointestinal disorders
Constipation | 5 | 7 | 1
Dry mouth | 0 | 7 | 1
Dyspepsia | 6 | 6 | 0
Nausea | 3 | 4 | 5
Toothache | 1 | 3 | 0
Salivary hypersecretion | 4 | 1 | 0
General disorders and administration site conditions
Fatigue [Fatigue includes fatigue and asthenia.] | 3 | 9 | 0
Edema peripheral | 2 | 3 | 1
Pain | 4 | 1 | 0
Pyrexia | 2 | 1 | 0
Infections and infestations
Upper respiratory tract infection | 2 | 0 | 1
Investigations
Weight increased | 5 | 4 | 2
Weight decreased | 4 | 1 | 1
Musculoskeletal and connective tissue disorders
Pain in extremity | 6 | 2 | 1
Nervous system disorders
Headache | 15 | 21 | 12
Parkinsonism [Parkinsonism includes extrapyramidal disorder, musculoskeletal stiffness, muscle rigidity, and bradykinesia.] | 8 | 15 | 9
Dizziness | 7 | 11 | 6
Akathisia [Akathisia includes akathisia and restlessness.] | 4 | 11 | 6
Sedation [Sedation includes sedation and somnolence.] | 5 | 6 | 3
Tremor | 0 | 3 | 0
Syncope | 2 | 1 | 0
Hypoesthesia | 2 | 0 | 0
Respiratory, thoracic and mediastinal disorders
Cough | 4 | 2 | 3
Sinus congestion | 2 | 0 | 0
Skin and subcutaneous tissue disorders
Acne | 2 | 2 | 0
Dry skin | 2 | 0 | 0

Adverse Reactions in Double-Blind, Placebo-Controlled Clinical Trials – Bipolar Disorder

Table 5 lists the adverse reactions reported in 2% or more of risperidone long-acting injection (intramuscular)-treated patients in the 24-month double-blind, placebo-controlled treatment period of the trial assessing the efficacy and safety of risperidone long-acting injection (intramuscular) when administered as monotherapy for maintenance treatment in patients with Bipolar I Disorder.

Table 5. Adverse Reactions in ≥2% of Adult Patients with Bipolar I Disorder Treated with Risperidone Long-acting Injection (intramuscular) as Monotherapy in a 24-Month Double-Blind, Placebo-Controlled Trial
System/Organ Class Adverse Reaction | Risperidone Long-acting Injection (intramuscular) (N=154) % | Placebo (N=149) %
Investigations
Weight increased | 5 | 1
Nervous system disorders
Dizziness | 3 | 1
Vascular disorders
Hypertension | 3 | 1

Table 6 lists the adverse reactions reported in 4% or more of patients in the 52-week double-blind, placebo-controlled treatment phase of a trial assessing the efficacy and safety of risperidone long-acting injection as adjunctive maintenance treatment in patients with bipolar disorder.

Table 6. Adverse Reactions Occurring in ≥ 4% of Adult Patients with Bipolar I Disorder Treated with Risperidone Long-acting Injection (intramuscular) as Adjunctive Therapy in a 52-Week Double-Blind, Placebo-Controlled Trial
System/Organ Class Adverse Reaction | Risperidone Long-acting Injection (intramuscular) + Treatment as Usual [Patients received double-blind risperidone long-acting injection (intramuscular) or placebo in addition to continuing their treatment as usual, which included mood stabilizers, antidepressants, and/or anxiolytics.] (N=72) % | Placebo + Treatment as Usual (N=67) %
General disorders and administration site conditions
Gait abnormal | 4 | 0
Infections and infestations
Upper respiratory tract infection | 6 | 3
Investigations
Weight increased | 7 | 1
Metabolism and nutrition disorders
Decreased appetite | 6 | 1
Increased appetite | 4 | 0
Musculoskeletal and connective tissue disorders
Arthralgia | 4 | 3
Nervous system disorders
Tremor | 24 | 16
Parkinsonism [Parkinsonism includes muscle rigidity, hypokinesia, cogwheel rigidity, and bradykinesia.] | 15 | 6
Dyskinesia [Dyskinesia includes muscle twitching and dyskinesia.] | 6 | 3
Sedation [Sedation includes sedation and somnolence.] | 7 | 1
Disturbance in attention | 4 | 0
Reproductive system and breast disorders
Amenorrhea | 4 | 1
Respiratory, thoracic and mediastinal disorders
Cough | 4 | 1

Other Adverse Reactions Observed During the Clinical Trial Evaluation of Risperidone

The following additional adverse reactions occurred in < 2% of the risperidone long-acting injection (intramuscular)-treated patients in the above schizophrenia double-blind, placebo-controlled trial dataset, in < 2% of the risperidone long-acting injection (intramuscular) -treated patients in the above double-blind, placebo-controlled period of the monotherapy bipolar disorder trial dataset, or in < 4% of the risperidone long-acting injection (intramuscular)-treated patients in the above double-blind, placebo-controlled period of the adjunctive treatment bipolar disorder trial dataset. The following also includes additional adverse reactions reported at any frequency in risperidone long-acting injection (intramuscular)-treated patients who participated in the open-label phases of the above bipolar disorder studies and in other studies, including double-blind, active controlled, and open-label studies in schizophrenia and bipolar disorder.

Blood and lymphatic system disorders: anemia, neutropenia

Cardiac disorders: tachycardia, atrioventricular block first degree, palpitations, sinus bradycardia, bundle branch block left, bradycardia, sinus tachycardia, bundle branch block right

Ear and labyrinth disorders: ear pain, vertigo

Endocrine disorders: hyperprolactinemia

Eye disorders: conjunctivitis, visual acuity reduced

Gastrointestinal disorders: diarrhea, vomiting, abdominal pain upper, abdominal pain, stomach discomfort, gastritis

General disorders and administration site conditions: injection site pain, chest discomfort, chest pain, influenza like illness, sluggishness, malaise, induration, injection site induration, injection site swelling, injection site reaction, face edema

Immune system disorders: hypersensitivity

Infections and infestations: nasopharyngitis, influenza, bronchitis, urinary tract infection, rhinitis, respiratory tract infection, ear infection, pneumonia, lower respiratory tract infection, pharyngitis, sinusitis, viral infection, infection, localized infection, cystitis, gastroenteritis, subcutaneous abscess

Injury and poisoning: fall, procedural pain

Investigations: blood prolactin increased, alanine aminotransferase increased, electrocardiogram abnormal, gamma-glutamyl transferase increased, blood glucose increased, hepatic enzyme increased, aspartate aminotransferase increased, electrocardiogram QT prolonged, glucose urine present

Metabolism and nutritional disorders: anorexia, hyperglycemia

Musculoskeletal, connective tissue and bone disorders: posture abnormal, myalgia, back pain, buttock pain, muscular weakness, neck pain, musculoskeletal chest pain

Nervous system disorders: coordination abnormal, dystonia, tardive dyskinesia, drooling, paresthesia, dizziness postural, convulsion, akinesia, hypokinesia, dysarthria

Psychiatric disorders: insomnia, agitation, anxiety, sleep disorder, depression, initial insomnia, libido decreased, nervousness

Renal and urinary disorders: urinary incontinence

Reproductive system and breast disorders: galactorrhea, oligomenorrhea, erectile dysfunction, sexual dysfunction, ejaculation disorder, gynecomastia, breast discomfort, menstruation irregular, menstruation delayed, menstrual disorder, ejaculation delayed

Respiratory, thoracic and mediastinal disorders: nasal congestion, pharyngolaryngeal pain, dyspnea, rhinorrhea

Skin and subcutaneous tissue disorders: rash, eczema, pruritus generalized, pruritus

Vascular disorders: hypotension, orthostatic hypotension

Additional Adverse Reactions Reported with Oral Risperidone

Additional adverse reactions that have been reported during the clinical trial evaluation of oral risperidone, regardless of frequency of occurrence, include the following:

Blood and Lymphatic Disorders: granulocytopenia

Cardiac Disorders: atrioventricular block

Ear and Labyrinth Disorders: tinnitus

Eye Disorders: ocular hyperemia, eye discharge, eye rolling, eyelid edema, eye swelling, eyelid margin crusting, dry eye, lacrimation increased, photophobia, glaucoma

Gastrointestinal Disorders: abdominal pain upper, dysphagia, fecaloma, abdominal discomfort, fecal incontinence, lip swelling, cheilitis, aptyalism

General Disorders: thirst, feeling abnormal, gait disturbance, pitting edema, edema, chills, discomfort, generalized edema, drug withdrawal syndrome, peripheral coldness

Immune System Disorders: drug hypersensitivity

Infections and Infestations: tonsillitis, eye infection, cellulitis, otitis media, onychomycosis, acarodermatitis, bronchopneumonia, respiratory tract infection, tracheobronchitis, otitis media chronic

Investigations: body temperature increased, heart rate increased, eosinophil count increased, WBC count decreased, hemoglobin decreased, blood creatine phosphokinase increased, hematocrit decreased, body temperature decreased, blood pressure decreased, transaminases increased

Metabolism and Nutrition Disorders: polydipsia

Musculoskeletal, Connective Tissue, and Bone Disorders: joint swelling, joint stiffness, rhabdomyolysis, torticollis

Nervous System Disorders: hypertonia, balance disorder, dysarthria, unresponsive to stimuli, depressed level of consciousness, movement disorder, hypokinesia, parkinsonian rest tremor, transient ischemic attack, cerebrovascular accident, masked facies, speech disorder, loss of consciousness, muscle contractions involuntary, akinesia, cerebral ischemia, cerebrovascular disorder, neuroleptic malignant syndrome (NMS), diabetic coma, head titubation

Psychiatric Disorders: blunted affect, confusional state, middle insomnia, listlessness, anorgasmia

Renal and Urinary Disorders: enuresis, dysuria, pollakiuria

Reproductive System and Breast Disorders: vaginal discharge, retrograde ejaculation, ejaculation disorder, ejaculation failure, breast enlargement

Respiratory, Thoracic, and Mediastinal Disorders: epistaxis, wheezing, pneumonia aspiration, dysphonia, productive cough, pulmonary congestion, respiratory tract congestion, rales, respiratory disorder, hyperventilation, nasal edema

Skin and Subcutaneous Tissue Disorders: erythema, skin discoloration, skin lesion, skin disorder, rash erythematous, rash papular, hyperkeratosis, dandruff, seborrheic dermatitis, rash generalized, rash maculopapular

Vascular Disorders: flushing

Discontinuations Due to Adverse Reactions

Schizophrenia

Approximately 11% (22/202) of risperidone long-acting (intramuscular)-treated patients in the 12-week double-blind, placebo-controlled schizophrenia trial discontinued treatment due to an adverse reaction, compared with 13% (13/98) who received placebo. The adverse reactions associated with discontinuation in two or more risperidone long-acting injection (intramuscular)-treated patients were agitation (3%), depression (2%), anxiety (1%), and akathisia (1%).

Bipolar Disorder

In the 24-month double-blind, placebo-controlled treatment period of the trial assessing the efficacy and safety of risperidone long-acting injection (intramuscular) monotherapy for maintenance treatment in patients with bipolar I disorder, 1 (0.6%) of 154 risperidone long-acting injection (intramuscular)-treated patients discontinued due to an adverse reaction (hyperglycemia).

In the 52-week double-blind phase of the placebo-controlled trial in which risperidone long-acting injection (intramuscular) was administered as adjunctive therapy to patients with bipolar disorder in addition to continuing with their usual treatment, approximately 4% (3/72) of risperidone long-acting injection (intramuscular)-treated patients discontinued treatment due to an adverse event, compared with 1.5% (1/67) of placebo-treated patients. Adverse reactions associated with discontinuation in risperidone long-acting injection(intramuscular)-treated patients were hypokinesia (one patient) and tardive dyskinesia (one patient).

Dose Dependency of Adverse Reactions in Clinical Trials

Extrapyramidal Symptoms (EPS)

Two methods were used to measure EPS in the 12-week double-blind, placebo-controlled trial comparing three doses of risperidone long-acting injection (intramuscular) (25 mg, 50 mg, and 75 mg) with placebo in patients with schizophrenia: (1) the incidence of spontaneous reports of EPS symptoms; and (2) the change from baseline to endpoint on the total score (sum of the subscale scores for parkinsonism, dystonia, and dyskinesia) of the Extrapyramidal Symptom Rating Scale (ESRS).

The overall incidence of EPS-related adverse reactions (akathisia, dystonia, parkinsonism, and tremor) in patients treated with 25 mg risperidone long-acting injection (intramuscular)was comparable to that of patients treated with placebo; the incidence of EPS-related adverse reactions was higher in patients treated with 50 mg risperidone long-acting injection (intramuscular) (Table 4).

The median change from baseline to endpoint in total ESRS score showed no worsening in patients treated with risperidone long-acting injection (intramuscular) compared with patients treated with placebo: 0 (placebo group); -1 (25-mg group, significantly less than the placebo group); and 0 (50-mg group).

Dystonia

Symptoms of dystonia, prolonged abnormal contractions of muscle groups, may occur in susceptible individuals during the first few days of treatment. Dystonic symptoms include neck muscle spasms, sometimes progressing to tightness of the throat, swallowing difficulty, difficulty breathing, and/or protrusion of the tongue. While these symptoms can occur at low doses, they occur more frequently and with greater severity with high potency and at higher doses of first-generation antipsychotic drugs. An elevated risk of acute dystonia is observed in males and younger age groups.

Changes in ECG

The ECGs of 202 patients with schizophrenia treated with 25 mg or 50 mg risperidone long-acting injection (intramuscular) and 98 schizophrenic patients treated with placebo in the 12-week double-blind, placebo-controlled trial were evaluated. There were no statistically significant differences in QTc intervals (using Fridericia's and linear correction factors) during treatment with either risperidone long-acting injection (intramuscular)or placebo.

The ECGs of 227 patients with Bipolar I Disorder were evaluated in the 24-month double-blind, placebo-controlled period. There were no clinically relevant differences in QTc intervals (using Fridericia's and linear correction factors) during treatment with risperidone long-acting injection (intramuscular) compared to placebo.

The ECGs of 85 patients with bipolar disorder were evaluated in the 52-week double-blind, placebo-controlled trial. There were no statistically significant differences in QTc intervals (using Fridericia's and linear correction factors) during adjunctive treatment with either risperidone long-acting injection (intramuscular) (25 mg, 37.5 mg, or 50 mg) or placebo in addition to treatment as usual.

Pain Assessment and Local Injection Site Reactions

The mean intensity of injection pain reported by patients with schizophrenia using a visual analog scale (0 = no pain to 100 = unbearably painful) decreased in all treatment groups from the first to the last dose of risperidone long-acting injection (intramuscular) (placebo: 16.7 to 12.6; 25 mg: 12.0 to 9.0; 50 mg: 18.2 to 11.8). After the sixth injection (Week 10), investigator ratings indicated that 1% of patients treated with 25 mg or 50 mg risperidone long-acting injection (intramuscular) experienced redness, swelling, or induration at the injection site.

6.2 Postmarketing Experience

The following adverse reactions have been identified during post-approval use of risperidone. Because these reactions are reported voluntarily from a population of uncertain size, it is not possible to reliably estimate their frequency or establish causal relationship to a drug exposure. These adverse reactions include: agranulocytosis, alopecia, anaphylactic reaction, angioedema, atrial fibrillation, blood cholesterol increased, blood triglycerides increased, catatonia, diabetes mellitus, diabetic ketoacidosis in patients with impaired glucose metabolism, drug withdrawal syndrome neonatal, dysgeusia, hypoglycemia, hypothermia, ileus, inappropriate antidiuretic hormone secretion, intestinal obstruction, jaundice, mania, pancreatitis, priapism, QT prolongation, sleep apnea syndrome, somnambulism, Stevens-Johnson syndrome and toxic epidermal necrolysis (SJS/TEN), thrombocytopenia, thrombotic thrombocytopenic purpura, urinary retention, and water intoxication. In addition, the following adverse reactions have been observed during post-approval use of risperidone long-acting injection (intramuscular): cerebrovascular disorders, including cerebrovascular accidents, and diabetes mellitus aggravated.

Retinal artery occlusion after use of risperidone long-acting injection (intramuscular) has been reported during postmarketing surveillance. This was reported in the presence of abnormal arteriovenous anastomosis.

Serious injection site reactions including abscess, cellulitis, cyst, hematoma, necrosis, nodule, and ulcer have been reported with risperidone long-acting injection (intramuscular) during postmarketing surveillance. Isolated cases required surgical intervention.

Very rarely, cases of anaphylactic reaction after administration of risperidone long-acting injection (intramuscular) have been reported during postmarketing experience in patients who previously tolerated oral risperidone.

Postmarketing cases of extrapyramidal symptoms (dystonia and dyskinesia) have been reported in patients concomitantly taking methylphenidate and risperidone when there was an increase or decrease in dosage, initiation, or discontinuation of either or both medications.

7 DRUG INTERACTIONS

7.1 Drugs Having Clinically Significant Interactions with RYKINDO

The interactions of RYKINDO with co-administration of other drugs have not been studied. The drug interaction data provided in this section is based on studies with oral risperidone.

Clinically significant drug interactions with RYKINDO are included in Table 7.

Table 7. Clinically Significant Drug Interactions with RYKINDO
Strong CYP2D6 Inhibitors
Clinical Impact | Concomitant use of RYKINDO with strong CYP2D6 inhibitors may increase the plasma concentration of risperidone and lower the concentration of 9-hydroxyrisperidone, a major active metabolite of risperidone [see Clinical Pharmacology (12.3)].
Intervention | When initiation of strong CYP2D6 inhibitors is considered, patients may be placed on a lower dose of RYKINDO between 2 to 4 weeks before the planned start of strong CYP2D6 inhibitors to adjust for the expected increase in plasma concentrations of risperidone. When a strong CYP2D6 inhibitor is initiated in patients receiving the recommended dose of 25 mg RYKINDO, it is recommended to continue treatment with the 25 mg dose unless clinical judgment necessitates either lowering the dose to 12.5 mg, in which case a different risperidone long-acting injection intramuscular formulation should be used, or interruption of RYKINDO treatment. The effects of discontinuation of strong CYP2D6 inhibitors on the pharmacokinetics of risperidone and 9-hydroxyrisperidone have not been studied [see Dosage and Administration (2.7) ].
Strong CYP3A4 Inducers
Clinical Impact | Co-administration of a strong CYP3A4 inducer with RYKINDO may cause decreases in the combined plasma concentrations of risperidone and 9-hydroxyrisperidone, which could lead to decreased efficacy of RYKINDO® treatment [see Clinical Pharmacology (12.3)].
Intervention | When initiating therapy with a strong CYP3A4 inducer, patients should be closely monitored during the first 4 to 8 weeks because the dose of RYKINDO may need to be adjusted. A dose increase or additional oral risperidone may need to be considered. When discontinuing a strong CYP3A4 inducer, the dosage of RYKINDO should be re-evaluated and decreased, if necessary. Patients may be placed on a lower dose of RYKINDO between 2 to 4 weeks before the planned discontinuation of CYP3A4 inducers to adjust for the expected increase in plasma concentrations of risperidone plus 9-hydroxyrisperidone. For patients treated with the recommended dose of 25 mg RYKINDO and discontinuing from a CYP3A4 enzyme inducer, it is recommended to continue treatment with the 25-mg dose unless clinical judgment necessitates either lowering the RYKINDO dose to 12.5 mg, in which case a different risperidone long-acting injection intramuscular formulation should be used, or interruption of RYKINDO treatment. [see Dosage and Administration (2.7)].
Centrally-Acting Drugs and Alcohol
Clinical Impact | Nervous system disorders may be exacerbated due to additive pharmacological effects associated with the concomitant use of centrally-acting drugs, including alcohol.
Intervention | Use caution when RYKINDO is administered in combination with other centrally-acting drugs or alcohol.
Hypotensive Agents
Clinical Impact | Because of its potential for inducing hypotension, RYKINDO may enhance the hypotensive effects of other therapeutic agents with this potential.
Intervention | Use caution when RYKINDO is administered in combination with other therapeutic agents with hypotensive effects.
Dopamine Agonists
Clinical Impact | RYKINDO may antagonize the effects of levodopa and dopamine agonists.
Intervention | Caution should be used when RYKINDO is administered in combination with levodopa and dopamine agonists.
Methylphenidate
Clinical Impact: | Concomitant use with methylphenidate, when there is change in dosage of either medication, may increase the risk of extrapyramidal symptoms (EPS) [see Adverse Reactions (6.2)].
Intervention: | Monitor for symptoms of EPS with concomitant use of RYKINDO and methylphenidate.

7.2 Drugs Having No Clinically Important Interactions with RYKINDO

Based on pharmacokinetic studies with oral risperidone, no dosage adjustment of RYKINDO® is required when administered concomitantly with amitriptyline, cimetidine, ranitidine, clozapine, topiramate and moderate CYP3A4 inhibitors (erythromycin). Additionally, no dosage adjustment is necessary for lithium, valproate, topiramate, digoxin and CYP2D6 substrates (donepezil and galantamine) when co-administered with RYKINDO [see Clinical Pharmacology (12.3)].

8 USE IN SPECIFIC POPULATIONS

8.1 Pregnancy

Pregnancy Exposure Registry

There is a pregnancy exposure registry that monitors pregnancy outcomes in women exposed to atypical antipsychotics, including RYKINDO, during pregnancy. Healthcare providers are encouraged to register patients by contacting the National Pregnancy Registry for Atypical Antipsychotics at 1-866-961-2388 or online at http://womensmentalhealth.org/clinicaland-research-programs/pregnancyregistry/.

Risk Summary

Neonates exposed to antipsychotic drugs during the third trimester of pregnancy are at risk for extrapyramidal and/or withdrawal symptoms following delivery (see Clinical Considerations). Overall, available data from published epidemiologic studies of pregnant women exposed to risperidone have not established a drug-associated risk of major birth defects, miscarriage, or adverse maternal or fetal outcomes (see Data). There are risks to the mother associated with untreated schizophrenia or bipolar I disorder and with exposure to antipsychotics, including RYKINDO, during pregnancy (see Clinical Considerations). Risperidone has been detected in plasma in adult subjects up to 6 weeks after a single-dose of RYKINDO [see Clinical Pharmacology (12.3)]. The clinical significance of RYKINDO administered before or during pregnancy is unknown.

Oral administration of risperidone to pregnant mice caused cleft palate at doses 3 to 4 times the maximum recommended human dose (MRHD) with maternal toxicity observed at 4 times the MRHD based on mg/m^2 body surface area. Risperidone was not teratogenic in rats or rabbits at doses up to 6 times the MRHD based on mg/m^2 body surface area. Increased incidence of stillbirths and decreased birth weight occurred after oral risperidone administration to pregnant rats at 1.5 times the MRHD based on mg/m^2 body surface area. Learning was impaired in the offspring of dams dosed at 0.6-times the MRHD and offspring mortality increased at maternal doses 0.1 to 3 times the MRHD based on mg/m^2 body surface area.

The estimated background risk of major birth defects and miscarriage for the indicated population is unknown. All pregnancies have a background risk of birth defect, loss, or other adverse outcomes. In the U.S. general population, the estimated background risk of major birth defects and miscarriage in clinically recognized pregnancies is 2% to 4% and 15% to 20%, respectively.

Clinical Considerations

Disease-associated maternal and/or embryo/fetal risk

There is a risk to the mother from untreated schizophrenia or bipolar I disorder, including increased risk of relapse, hospitalization, and suicide. Schizophrenia and bipolar I disorder are associated with increased adverse perinatal outcomes, including preterm birth. It is not known if this is a direct result of the illness or other comorbid factors.

Fetal/Neonatal Adverse Reactions

Extrapyramidal and/or withdrawal symptoms (including agitation, hypertonia, hypotonia, tremor, somnolence, respiratory distress, and feeding disorder) have been reported in neonates who were exposed to antipsychotic drugs, including risperidone, during the third trimester of pregnancy. These symptoms varied in severity. Monitor neonates for extrapyramidal and/or withdrawal symptoms and manage symptoms appropriately. Some neonates recovered within hours or days without specific treatment; others required prolonged hospitalization.

Data

Human Data

Published data from observational studies, birth registries, and case reports on the use of atypical antipsychotics during pregnancy do not show a clear association between antipsychotics and major birth defects. A prospective observational study including 6 women treated with risperidone demonstrated placental passage of risperidone. A retrospective cohort study from a Medicaid database of 9258 women exposed to antipsychotics during pregnancy did not indicate an overall increased risk for major birth defects. There was a small increase in the risk of major birth defects (RR=1.26, 95% CI: 1.02-1.56) and of cardiac malformations (RR=1.26, 95% CI: 0.88-1.81) in a subgroup of 1566 women exposed to risperidone during the first trimester of pregnancy; however, there is no mechanism of action to explain the difference in malformation rates.

Animal Data

Oral administration of risperidone to pregnant mice during organogenesis caused cleft palate at 10 mg/kg/day or 3 times the MRHD of 16 mg/day based on mg/m^2 body surface area; maternal toxicity occurred at 4 times the MRHD. Risperidone was not teratogenic when administered orally to rats at 0.6 to 10 mg/kg/day and rabbits at 0.3 to 5 mg/kg/day which are up to 6 times the MRHD of 16 mg/day risperidone based on mg/m^2 body surface area. Learning was impaired in the offspring of rats dosed orally throughout pregnancy at 1 mg/kg/day which is 0.6 times the MRHD and neuronal cell death increased in fetal brains of rats dosed during pregnancy at 1 and 2 mg/kg/day which are 0.6 and 1.2 times the MRHD; postnatal development and growth of the offspring were also delayed.

Rat offspring mortality increased during the first 4 days of lactation when pregnant rats were dosed throughout gestation at 0.16 to 5 mg/kg/day which are 0.1 to 3 times the MRHD of 16 mg/day risperidone based on mg/m^2 body surface area. It is not known whether these deaths were due to a direct effect on the fetuses or pups or to effects on the dams; a no-effect dose could not be determined. The rate of stillbirths was increased at 2.5 mg/kg or 1.5 times the MRHD.

In a rat cross-fostering study, the number of live offspring was decreased, the number of stillbirths was increased, and the offspring birth weight was decreased in offspring of drug-treated pregnant rats. In addition, the number of deaths increased by Day 1 among offspring of drug-treated pregnant rats, regardless of whether or not the offspring were cross-fostered. Risperidone also appeared to impair maternal behavior in that offspring body weight gain and survival (from Day 1 to 4 of lactation) were reduced for offspring born to control but reared by drug-treated dams. All of these effects occurred at 5 mg/kg which is 3 times the MRHD and the only dose tested in the study.

8.2 Lactation

Risk Summary

Limited data from published literature reports the presence of risperidone and its metabolite, 9-hydroxyrisperidone, in human breast milk at relative infant doses ranging between 2.3% and 4.7% of the maternal weight-adjusted dose. There are reports of sedation, failure to thrive, jitteriness, and EPS (tremors and abnormal muscle movements) in breastfed infants exposed to risperidone (see Clinical Considerations). Risperidone has been detected in the plasma in adult subjects up to 6 weeks after a single-dose of RYKINDO [see Clinical Pharmacology (12.3)], and the clinical significance on the breastfed infant is not known. There is no information on the effects of risperidone on milk production. The developmental and health benefits of breastfeeding should be considered along with the mother's clinical need for RYKINDO and any potential adverse effects on the breastfed child from RYKINDO or from the mother's underlying condition.

Clinical Considerations

Infants exposed to RYKINDO through breastmilk should be monitored for excess sedation, failure to thrive, jitteriness, and EPS (tremors and abnormal muscle movements).

8.3 Females and Males of Reproductive Potential

Infertility

Females

Based on the pharmacologic action of risperidone (D2 receptor antagonism), treatment with RYKINDO may result in an increase in serum prolactin levels, which may lead to a reversible reduction in fertility in females of reproductive potential [see Warnings and Precautions (5.6) and Nonclinical Toxicology (13.1)].

8.4 Pediatric Use

Safety and effectiveness of RYKINDO have not been established in pediatric patients.

Juvenile Animal Toxicity Studies

Juvenile dogs were treated with oral risperidone from weeks 10 to 50 of age (equivalent to childhood through adolescence in humans) at doses of 0.31, 1.25, or 5 mg/kg/day (1.2, 3.4, or 13.5 times the MRHD of 6 mg/day for children, based on mg/m^2 body surface area). Bone length and density were decreased with a no-effect dose of 0.31 mg/kg/day; this dose produced plasma AUCs of risperidone and 9-hydroxyrisperidone combined that were similar to those in children and adolescents receiving the MRHD of 6 mg/day. In addition, sexual maturation was delayed at all doses in both males and females. The above effects showed little or no reversibility in females after a 12-week drug-free recovery period.

Juvenile rats treated with oral risperidone from days 12 to 50 of age (equivalent to the period of infancy through adolescence in humans) showed impaired learning and memory performance (reversible only in females) with a no-effect dose of 0.63 mg/kg/day (0.5 times the MRHD of 6 mg/day for children). This dose produced plasma AUCs of risperidone and 9-hydroxyrisperidone combined that were approximately half the AUCs observed in humans at the MRHD. No other consistent effects on neurobehavioral or reproductive development were seen in juvenile rats given up to the highest tested dose of 1.25 mg/kg/day which is 1 time the MRHD and produced plasma AUCs of risperidone plus paliperidone that were about two thirds of those observed in humans at the MRHD of 6mg/day of children.

8.5 Geriatric Use

In an open-label study, 57 clinically stable, geriatric patients (≥ 65 years old) with schizophrenia or schizoaffective disorder received risperidone long-acting injection (intramuscular) every 2 weeks for up to 12 months. In general, no differences in the tolerability of risperidone long-acting injection (intramuscular) were observed between otherwise healthy geriatric and younger patients.

Because geriatric patients exhibit a greater tendency for orthostatic hypotension than nonelderly patients, geriatric patients should be instructed in nonpharmacologic interventions that help to reduce the occurrence of orthostatic hypotension (e.g., sitting on the edge of the bed for several minutes before attempting to stand in the morning and slowly rising from a seated position). In addition, monitoring of orthostatic vital signs should be considered in geriatric patients for whom orthostatic hypotension is a concern [see Warnings and Precautions (5.7)].

Elderly patients with dementia-related psychosis treated with RYKINDO are at an increased risk of death compared to placebo. RYKINDO is not approved for the treatment of patients with dementia related psychosis [see Boxed Warning and Warnings and Precautions (5.1, 5.2)].

8.6 Renal Impairment

In patients with renal impairment, titrate with oral risperidone (up to at least 2 mg) prior to initiating treatment with RYKINDO [see Dosage and Administration (2.6)].

Although patients with renal impairment were not studied with RYKINDO, they may have reduced risperidone elimination compared to patients with normal renal function [see Clinical Pharmacology (12.3)].

8.7 Hepatic Impairment

In patients with hepatic impairment, titrate with oral risperidone (up to at least 2 mg) prior to initiating treatment with RYKINDO [see Dosage and Administration (2.6)].

Although patients with hepatic impairment were not studied in RYKINDO clinical trials, they may have a clinically significant increase in the free fraction of risperidone, possibly resulting in an enhanced effect [see Clinical Pharmacology (12.3)].

8.8 Patients with Parkinson's Disease or Dementia with Lewy Bodies

Patients with Parkinson's disease or dementia with Lewy bodies can experience increased sensitivity to RYKINDO. Manifestations can include confusion, obtundation, postural instability with frequent falls, extrapyramidal symptoms, and clinical features consistent with neuroleptic malignant syndrome.

10 OVERDOSAGE

Human Experience

In premarketing experience with oral risperidone, there were eight reports of acute risperidone overdosage with estimated doses ranging from 20 to 300 mg and no fatalities. In general, reported signs and symptoms were those resulting from an exaggeration of the drug's known pharmacological effects, i.e., drowsiness and sedation, tachycardia and hypotension, and EPS. In one case, hyponatremia, hypokalemia, prolonged QT, and widened QRS were observed after a patient took an estimated 240 mg of oral risperidone. In another case, a patient had a seizure after taking an estimated 36 mg of oral risperidone.

Postmarketing experience with oral risperidone included reports of acute overdose with estimated doses up to 360 mg. In general, the most frequently reported signs and symptoms were those resulting from an exaggeration of the drug's known pharmacological effects, i.e., drowsiness, sedation, tachycardia, hypotension, and EPS. Other postmarketing adverse reactions related to oral risperidone overdose included prolonged QT interval and convulsions. Torsade de pointes was reported in association with combined overdose of oral risperidone and paroxetine.

Management of Overdosage

In case of acute overdosage, establish and maintain an airway and ensure adequate oxygenation and ventilation. Cardiovascular monitoring should commence immediately and include continuous electrocardiographic monitoring to detect possible arrhythmias. If antiarrhythmic therapy is administered, disopyramide, procainamide, and quinidine carry a theoretical hazard of QT prolonging effects that might be additive to those of risperidone. Similarly, it is reasonable to expect that the alpha-blocking properties of bretylium might be additive to those of risperidone, resulting in problematic hypotension.

There is no specific antidote to risperidone. Therefore, appropriate supportive measures should be implemented. The possibility of multiple drug involvement should be considered. Hypotension and circulatory collapse should be treated with appropriate measures, such as intravenous fluids and/or sympathomimetic agents (epinephrine and dopamine should not be used, since beta stimulation may worsen hypotension in the setting of risperidone-induced alpha blockade). In cases of severe EPS, anticholinergic medication should be administered. Close medical supervision and monitoring should continue until the patient recovers.

Consider contacting the Poison Help line (1-800-222-1222) or medical toxicologist for additional overdosage management recommendations.

11 DESCRIPTION

RYKINDO contains risperidone, an atypical antipsychotic belonging to the chemical class of benzisoxazole derivatives. The chemical designation is 3-[2-[4-(6-fluoro-1,2-benzisoxazol-3-yl)piperidin-1-yl] ethyl]-2-methyl-6,7,8,9-tetrahydro-4H-pyrido[1,2-a]pyrimidin-4-one. Its molecular formula is C23H27FN4O2 and its molecular weight is 410.5 g/mol. The structural formula is:

Risperidone is practically insoluble in water, freely soluble in methylene chloride, and soluble in methanol and 0.1 N HCl. RYKINDO is provided as a single-dose kit consisting of: a vial containing a white to almost white powder, a pre-filled syringe containing 2 mL of a colorless, clear diluent, a vial adapter, and a needle (a 20 gauge 2-inch needle with needle protection device).

The vial contains a white to almost white sterile powder containing risperidone. The powder consists of risperidone, mannitol (5.38 mg/100 mg risperidone), polylactide-co-glycolide (PLGA) 5050 (24.2 mg/100 mg risperidone) and polylactide-co-glycolide (PLGA) 7525 (96.7 mg/100 mg risperidone).

The diluent is a sterile, clear, colorless, 2 mL solution. The diluent contains: 1.10 mg/mL citric acid monohydrate, 1.02 mg/mL dibasic sodium phosphate anhydrous, 1 mg/mL polysorbate 80, 9 mg/mL sodium carboxymethyl cellulose, 7.5 mg/mL sodium chloride, 0.54 mg/mL sodium hydroxide, and water.

RYKINDO (risperidone) for extended-release injectable suspension, for intramuscular use is, when fully mixed, a white suspension, available in strengths of 25 mg, 37.5 mg, or 50 mg.

12 CLINICAL PHARMACOLOGY

12.1 Mechanism of Action

The mechanism of action of risperidone in schizophrenia is unclear. The drug's therapeutic activity could be mediated through a combination of dopamine Type 2 (D2) and serotonin Type 2 (5HT2) receptor antagonism. The clinical effect from risperidone results from the combined concentrations of risperidone and its major active metabolite, 9-hydroxyrisperidone (paliperidone) [see Clinical Pharmacology (12.3)]. Antagonism at receptors other than D2 and 5HT2 may explain some of the other effects of risperidone.

12.2 Pharmacodynamics

Risperidone is a monoaminergic antagonist with high affinity (Ki of 0.12 to 7.3 nM) for the serotonin Type 2 (5HT2), dopamine Type 2 (D2), α1 and α2 adrenergic, and H1 histaminergic receptors. Risperidone shows low to moderate affinity (Ki of 47 to 253 nM) for the serotonin 5HT1C, 5HT1D, and 5HT1A receptors; weak affinity (Ki of 620 to 800 nM) for the dopamine D1 and haloperidol-sensitive sigma site; and no affinity (when tested at concentrations >10^-5 M) for cholinergic muscarinic or β1 and β2 adrenergic receptors.

12.3 Pharmacokinetics

Absorption

After a single intramuscular injection of RYKINDO, the release profile consists of an initial release of risperidone followed by a stable release phase of 2 to 4 weeks. The median time to peak concentration (Tmax) of risperidone and 9-hydroxyrisperidone combined are 14 and 17 days after administration of 25 mg and 50 mg of RYKINDO, respectively. Systemic exposures (AUC0-t and Cmax) of the active moiety increase in a dose proportional manner across the dosing range from 25 mg to 50 mg.

The combination of the release profile and the dosage regimen (intramuscular injections every 2 weeks) of RYKINDO results in sustained concentrations within the dosing interval (every 2 weeks). Steady-state plasma concentration levels are reached after 2 injections and can be maintained for 2 to 3 weeks after the last injection. Following multiple IM injections (25 mg every two weeks for five consecutive injections) in patients, the geometric mean ratios [RYKINDO to risperidone long-acting injection (intramuscular)] of risperidone and 9-hydroxyrisperidone combined were 102.33% for the Css-max and 94.08% for the AUCss-tau, and the 90% CIs of the ratios were within the 80% to 125% range.

Distribution

The volume of distribution of risperidone is 1-2 L/kg. In plasma, risperidone is bound to albumin and α1-acid glycoprotein. The plasma protein binding of risperidone is approximately 90%, and that of its major metabolite, 9-hydroxyrisperidone, is 77%. Neither risperidone nor 9-hydroxyrisperidone displaces the other from plasma binding sites. High therapeutic concentrations of sulfamethazine (100 mcg/mL), warfarin (10 mcg/mL), and carbamazepine (10 mcg/mL) caused only a slight increase in the free fraction of risperidone at 10 ng/mL and of 9-hydroxyrisperidone at 50 ng/mL, changes of unknown clinical significance.

Elimination

Metabolism

Risperidone is extensively metabolized in the liver. The main metabolic pathway is through hydroxylation of risperidone to 9-hydroxyrisperidone by the enzyme CYP2D6. A minor metabolic pathway is through N-dealkylation. The main metabolite, 9-hydroxyrisperidone, has similar pharmacological activity as risperidone. Consequently, the clinical effect of the drug results from the combined concentrations of risperidone plus 9-hydroxyrisperidone.

CYP2D6, also called debrisoquin hydroxylase, is responsible for metabolism of many neuroleptics, antidepressants, antiarrhythmics, and other drugs. CYP2D6 is subject to genetic polymorphism (about 6% to 8% of Caucasians, and a very low percentage of Asians, have little or no activity and are "poor metabolizers") and to inhibition by a variety of substrates and some non-substrates, notably quinidine. Extensive CYP2D6 metabolizers convert risperidone rapidly into 9-hydroxyrisperidone, whereas poor CYP2D6 metabolizers convert it much more slowly. Although extensive metabolizers have lower risperidone and higher 9-hydroxyrisperidone concentrations than poor metabolizers, the pharmacokinetics of risperidone and 9-hydroxyrisperidone combined, after single and multiple doses, are similar in extensive and poor metabolizers.

Excretion

Risperidone and its metabolites are eliminated via the urine and, to a much lesser extent, via the feces. In a mass balance study of a single 1 mg oral dose of ^14C-risperidone administered in solution to three healthy male volunteers, total recovery of radioactivity at 1 week was 84%, including 70% in the urine and 14% in the feces.

The apparent half-life (t½) of active moiety following RYKINDO administration is 3 to 6 days and associated with a monoexponential decline in plasma concentrations after a single dose. This t½ is related to the erosion of the sterile powder and subsequent absorption of risperidone after RYKINDO intramuscular administration.

The clearance of risperidone and risperidone plus 9-hydroxyrisperidone was 13.7 L/h and 5.0 L/h in extensive CYP2D6 metabolizers, and 3.3 L/h and 3.2 L/h in poor CYP 2D6 metabolizers, respectively. The elimination phase is completed approximately 6 weeks after the last injection.

Specific Populations

Patients with Renal Impairment

Clearance of the sum of risperidone and 9-hydroxyrisperidone decreased by 60% in patients with moderate to severe renal disease compared with young healthy subjects treated with oral risperidone. [see Dosage and Administration (2.6)].

Patients with Hepatic Impairment

While the pharmacokinetics of oral risperidone in subjects with liver disease were comparable to those in young healthy subjects, the mean free fraction of risperidone in plasma was increased by about 35% because of the diminished concentration of both albumin and α1-acid glycoprotein. Although patients with hepatic impairment were not studied in RYKINDO clinical trials, it is recommended that patients with hepatic impairment be carefully titrated on oral risperidone before treatment with RYKINDO [see Dosage and Administration (2.6)].

Geriatric Patients

In an open-label trial, steady-state concentrations of risperidone plus 9-hydroxyrisperidone in otherwise healthy elderly patients (≥ 65 years old) treated with risperidone long-acting injection (intramuscular) for up to 12 months fell within the range of values observed in otherwise healthy nonelderly patients. Dosing recommendations are the same for otherwise healthy elderly patients and nonelderly patients.

Racial or Ethnic Groups and Male and Female Patients

No specific pharmacokinetic study was conducted to investigate race and gender effects, but a population pharmacokinetic analysis with risperidone long-acting injection (intramuscular) did not identify important differences in the disposition of risperidone due to gender (whether or not corrected for body weight) or race.

Drug Interaction Studies

Clinical Studies

The interactions of RYKINDO with co-administration of other drugs have not been systematically evaluated in humans. The drug interaction data provided in this section is based primarily on studies with oral risperidone. Effects of other drugs on the exposures of risperidone, 9-hydroxyrisperidone and total active moiety as well as the effects of risperidone on the exposures of other drugs are summarized below.

Effects of Other Drugs on Risperidone, 9-hydroxyrisperidone and Total Active Moiety Pharmacokinetics

Strong CYP2D6 Inhibitors (Fluoxetine and Paroxetine)

Fluoxetine (20 mg once daily) and paroxetine (20 mg once daily), potent CYP2D6 inhibitors, have been shown to increase the plasma concentration of risperidone by 2.5- to 2.8-fold and 3- to 9-fold, respectively. Fluoxetine did not affect the plasma concentration of 9-hydroxyrisperidone. Paroxetine lowered the concentration of 9-hydroxyrisperidone by about 10%. The effects of discontinuation of concomitant fluoxetine or paroxetine therapy on the pharmacokinetics of risperidone and 9-hydroxyrisperidone have not been studied [see Dosage and Administration (2.8) and Drug Interactions (7.1)].

Moderate CYP3A4 Inhibitor (Erythromycin)

There was no significant interaction between oral risperidone and erythromycin, a moderate CYP3A4 inhibitor.

Strong CYP3A4 Inducer (Carbamazepine)

Carbamazepine co-administration with oral risperidone decreased the steady-state plasma concentrations of risperidone and 9-hydroxyrisperidone by about 50%. Plasma concentrations of carbamazepine were not affected. Co-administration of other known CYP3A4 enzyme inducers (e.g., phenytoin, rifampin, and phenobarbital) with risperidone may cause similar decreases in the combined plasma concentrations of risperidone and 9-hydroxyrisperidone, which could lead to decreased efficacy of RYKINDO treatment [see Dosage and Administration (2.8) and Drug Interactions (7.1)].

Amitriptyline, Cimetidine, Ranitidine, Clozapine

Clinically meaningful pharmacokinetic interaction between RYKINDO and other drugs, such as amitriptyline, cimetidine, ranitidine and clozapine, is not expected.

Amitriptyline did not affect the pharmacokinetics of risperidone or of risperidone and 9- hydroxyrisperidone combined following concomitant administration with oral risperidone. Cimetidine and ranitidine increased the bioavailability of oral risperidone by 64% and 26%, respectively. However, cimetidine did not affect the AUC of risperidone and 9- hydroxyrisperidone combined, whereas ranitidine increased the AUC of risperidone and 9-hydroxyrisperidone combined by 20%. Chronic administration of clozapine with risperidone may decrease the clearance of risperidone.

Effects of Oral Risperidone on Pharmacokinetics of Other Drugs

Lithium

Repeated doses of oral risperidone (3 mg twice daily) did not affect the exposure (AUC) or peak plasma concentrations (Cmax) of lithium (n = 13).

Valproate

Repeated doses of oral risperidone (4 mg once daily) did not affect the pre-dose or average plasma concentrations and exposure (AUC) of valproate (1000 mg/day in three divided doses) compared to placebo (n = 21). However, there was a 20% increase in valproate peak plasma concentration (Cmax) after concomitant administration of oral risperidone.

Topiramate

Oral risperidone administered at doses from 1 to 6 mg/day concomitantly with topiramate 400 mg/day resulted in a 23% decrease in risperidone Cmax and a 33% decrease in risperidone AUC0-12 hour at steady state. Minimal reductions in the exposure to risperidone and 9-hydroxyrisperidone combined, and no change for 9-hydroxyrisperidone were observed. This interaction is unlikely to be of clinical significance. There was no clinically relevant effect of oral risperidone on the pharmacokinetics of topiramate.

Digoxin

Oral risperidone (0.25 mg twice daily) did not show a clinically relevant effect on the pharmacokinetics of digoxin.

Drugs Metabolized by CYP2D6

In vitro studies indicate that risperidone is a relatively weak inhibitor of CYP2D6. Therefore, RYKINDO® is not expected to substantially inhibit the clearance of drugs that are metabolized by this enzymatic pathway. In drug interaction studies, oral risperidone did not significantly affect the pharmacokinetics of donepezil and galantamine, which are metabolized by CYP2D6.

13 NONCLINICAL TOXICOLOGY

13.1 Carcinogenesis, Mutagenesis, Impairment of Fertility

Carcinogenesis - Oral

Risperidone was administered in the diet at doses of 0.63, 2.5, and 10 mg/kg for 18 months to mice and for 25 months to rats. These doses are equivalent to approximately 0.2, 0.75, and 3 times (mice) and 0.4, 1.5, and 6 times (rats) the MRHD of 16 mg/day, based on mg/m^2 body surface area. A maximum tolerated dose was not achieved in male mice. There was a significant increase in pituitary gland adenomas, endocrine pancreatic adenomas, and mammary gland adenocarcinomas. Table 8 summarizes the multiples of the human dose on a mg/m^2 (mg/kg) basis at which these tumors occurred.

Table 8. Summary of Tumor Occurrence at Multiples of the MRHD [MRHD = maximum recommended human dose on a mg/ m^2 (mg/kg) basis] with Oral Risperidone Dosing in Mice and Rats
Tumor Type | Species | Sex | Multiples of the MRHD in mg/m^2 (mg/kg)
Tumor Type | Species | Sex | Lowest Effect Level | Highest No-Effect Level
Pituitary adenomas | Mouse | Female | 0.75 (9.4) | 0.2 (2.4)
Endocrine pancreas adenomas | Rat | Male | 1.5 (9.4) | 0.4 (2.4)
Mammary gland adenocarcinomas | Mouse | Female | 0.2 (2.4) | None
Mammary gland adenocarcinomas | Rat | Female | 0.4 (2.4) | None
Mammary gland adenocarcinomas | Rat | Male | 6.0 (37.5) | 1.5 (9.4)
Mammary gland neoplasm (total) | Rat | Male | 1.5 (9.4) | 0.4 (2.4)

Antipsychotic drugs chronically elevate prolactin levels in rodents. Serum prolactin levels were not measured during the risperidone carcinogenicity studies; however, measurements during subchronic toxicity studies showed that risperidone elevated serum prolactin levels by 5- to 6- fold in mice and rats at the same doses used in the carcinogenicity studies. An increase in mammary, pituitary, and endocrine pancreas neoplasms were found in rodents after chronic administration of other antipsychotic drugs. These neoplasms were considered to be prolactin-mediated. The clinical relevance of the findings of prolactin-mediated endocrine tumors in rodents is unclear [see Warnings and Precautions (5.6)].

Carcinogenesis - Intramuscular

Risperidone was evaluated in a 24-month carcinogenicity study in which SPF Wistar rats were treated every 2 weeks with intramuscular (IM) injections of either 5 mg/kg or 40 mg/kg of risperidone. These doses are 1 and 8 times the MRHD (50 mg) on a mg/m^2 basis. A control group received injections of 0.9% NaCl, and a vehicle control group was injected with placebo. There was a significant increase in pituitary gland adenomas, endocrine pancreas adenomas, and adrenomedullary pheochromocytomas at 8 times the IM MRHD on a mg/m^2 basis. The incidence of mammary gland adenocarcinomas was significantly increased in female rats at both doses (1 and 8 times the IM MRHD on a mg/m^2 basis). A significant increase in renal tubular tumors (adenoma, adenocarcinomas) was observed in male rats at 8 times the IM MRHD on a mg/m^2 basis. Plasma exposures (AUC) in rats were 0.3 and 2 times (at 5 and 40 mg/kg, respectively) the expected plasma exposure (AUC) at the IM MRHD.

Dopamine D2 receptor antagonists have been shown to chronically elevate prolactin levels in rodents. Serum prolactin levels were not measured during the carcinogenicity studies of oral risperidone; however, measurements taken during subchronic toxicity studies showed that oral risperidone elevated serum prolactin levels by 5- to 6-fold in mice and rats at the same doses used in the oral carcinogenicity studies. Serum prolactin levels increased in a dose-dependent manner up to 6- and 1.5-fold in male and female rats, respectively, at the end of the 24-month treatment with risperidone every 2 weeks IM. Increases in the incidence of pituitary gland, endocrine pancreas, and mammary gland neoplasms have been found in rodents after chronic administration of other antipsychotic drugs and may be prolactin-mediated.

The relevance for human risk of the findings of prolactin-mediated endocrine tumors in rodents is unknown [see Warnings and Precautions (5.6)].

Mutagenesis

No evidence of mutagenic or clastogenic potential for risperidone was found in the in vitro tests of Ames gene mutation, the mouse lymphoma assay, rat hepatocyte DNA-repair assay, the chromosomal aberration test in human lymphocytes, Chinese hamster ovary cells, or in the in vivo micronucleus test in mice, and the sex-linked recessive lethal test in Drosophila.

In addition, no evidence of mutagenic potential was found in the in vitro Ames reverse mutation test for risperidone long-acting injection (intramuscular).

Impairment of Fertility

Oral risperidone (0.16 to 5 mg/kg) impaired mating, but not fertility, in rat reproductive studies at doses between 0.1 and 3 times the oral maximum recommended human dose (MRHD of 16 mg/day) based on a mg/m^2 body surface area. The effect appeared to be in females since impaired mating behavior was not noted in the male fertility study. In a subchronic study in Beagle dogs in which oral risperidone was administered at doses of 0.31 to 5 mg/kg, sperm motility and concentration were decreased at doses between 0.6 and 10 times the oral MRHD on a mg/m^2 basis. Dose-related decreases were also noted in serum testosterone at the same doses. Serum testosterone and sperm values partially recovered but remained decreased after treatment discontinuation. A no-effect dose could not be determined in either rat or dog.

14 CLINICAL STUDIES

14.1 Schizophrenia

The effectiveness of RYKINDO in the treatment of schizophrenia is based on an adequate and well-controlled study with risperidone long-acting injection (intramuscular). The effectiveness of risperidone long-acting injection (intramuscular) was established, in part, on the basis of the established effectiveness of the oral formulation of risperidone as well as in a 12-week, placebo-controlled trial in adult inpatients and outpatients who met the DSM-IV criteria for schizophrenia. The results of the adequate and well-controlled study are presented below.

Efficacy data were obtained from 400 patients with schizophrenia who were randomized to receive injections of 25 mg, 50 mg, or 75 mg risperidone long-acting injection (intramuscular) or placebo every 2 weeks. During a 1-week run-in period, patients were discontinued from other antipsychotics and were titrated to a dose of 4 mg oral risperidone. Patients who received risperidone long-acting injection (intramuscular) were given doses of oral risperidone (2 mg for patients in the 25-mg group, 4 mg for patients in the 50-mg group, and 6 mg for patients in the 75-mg group) for 3 weeks after the first injection to provide therapeutic plasma concentrations until the main release phase of risperidone from the injection site had begun. Patients who received placebo injections were given placebo tablets.

Efficacy was evaluated using the Positive and Negative Syndrome Scale (PANSS), a validated, multi-item inventory, composed of five subscales to evaluate positive symptoms, negative symptoms, disorganized thoughts, uncontrolled hostility/excitement, and anxiety/depression.

The primary efficacy variable in this trial was change from baseline to endpoint in the total PANSS score. The mean total PANSS score at baseline for schizophrenic patients in this study was 81.5.

Total PANSS scores showed significant improvement in the change from baseline to endpoint in schizophrenic patients treated with each dose of risperidone long-acting injection (intramuscular) (25 mg, 50 mg, or 75 mg) compared with patients treated with placebo. While there were no statistically significant differences between the treatment effects for the three dose groups, the effect size for the 75 mg dose group was actually numerically less than that observed for the 50 mg dose group.

Subgroup analyses did not indicate any differences in treatment outcome as a function of age, race, or gender.

14.2 Bipolar Disorder - Monotherapy

The effectiveness of RYKINDO for the maintenance treatment of bipolar I disorder is based on an adequate and well-controlled study with risperidone long-acting injection (intramuscular). The efficacy of risperidone long-acting injection (intramuscular) was established in a multicenter, double-blind, placebo-controlled study of adult patients who met DSM-IV criteria for Bipolar Disorder Type I, who were stable on medications or experiencing an acute manic or mixed episode. The results of the adequate and well-controlled study are presented below.

A total of 501 patients were treated during a 26-week open-label period with the risperidone long-acting injection (intramuscular) (starting dose of 25 mg, and titrated, if deemed clinically desirable, to 37.5 mg or 50 mg; in patients not tolerating the 25 mg dose, the dose could be reduced to 12.5 mg). In the open-label phase, 303 (60%) patients were judged to be stable and were randomized to double-blind treatment with either the same dose of risperidone long-acting injection (intramuscular) or placebo and monitored for relapse. The primary endpoint was time to relapse to any mood episode (depression, mania, hypomania, or mixed).

Time to relapse was delayed in patients receiving risperidone long-acting injection (intramuscular) monotherapy compared with patients receiving placebo. The majority of relapses were due to manic rather than depressive symptoms. Based on their bipolar disorder history, subjects entering this study had, on average, more manic episodes than depressive episodes.

14.3 Bipolar Disorder - Adjunctive Therapy

The effectiveness of RYKINDO as an adjunct to treatment with lithium or valproate for the maintenance treatment of bipolar I disorder is based on an adequate and well-controlled study of risperidone long-acting injection (intramuscular). The results of the adequate and well-controlled study are presented below.

The efficacy of risperidone long-acting injection (intramuscular) was established in a multi-center, randomized, double-blind, placebo-controlled study of adult patients who met DSM-IV criteria for Bipolar Disorder Type I and who experienced at least 4 episodes of mood disorder requiring psychiatric/clinical intervention in the previous 12 months, including at least 2 episodes in the 6 months prior to the start of the study.

A total of 240 patients were treated during a 16-week open-label period with risperidone long-acting injection (intramuscular) (starting dose of 25 mg, and titrated, if deemed clinically desirable, to 37.5 mg or 50 mg), as adjunctive therapy in addition to continuing their usual treatment for bipolar disorder, which consisted of mood stabilizers (primarily lithium and valproate), antidepressants, and/or anxiolytics. All oral antipsychotics were discontinued after the first three weeks after the initial injection of risperidone long-acting injection (intramuscular). In the open-label phase, 124 (51.7%) were judged to be stable for at least the last 4 weeks and were randomized to double-blind treatment with either the same dose of risperidone long-acting injection (intramuscular) or placebo in addition to continuing their usual treatment and monitored for relapse during a 52-week period. The primary endpoint was time to relapse to any new mood episode (depression, mania, hypomania, or mixed).

Time to relapse was delayed in patients receiving adjunctive therapy with risperidone long-acting injection (intramuscular) compared with patients receiving adjunctive therapy with placebo. The relapse types were about half depressive and half manic or mixed episodes.

16 HOW SUPPLIED/STORAGE AND HANDLING

How Supplied

RYKINDO (risperidone) for extended-release injectable suspension, for intramuscular use is, when fully mixed, a white suspension, available in strengths of 25 mg, 37.5 mg, or 50 mg. It is provided as a single-dose kit, consisting of: a vial containing a white to almost white powder, a pre-filled syringe containing 2 mL of a colorless, clear diluent, a vial adapter, and a needle (a 20 gauge 2-inch needle with needle protection device).

RYKINDO: 25-mg kit (NDC 72526-102-11): A white to almost white powder provided in a vial with a green flip-off cap (NDC 72526-202-01); a pre-filled syringe containing 2 mL of a colorless, clear diluent (NDC 72526-801-01); a needle; and a vial adapter.

RYKINDO: 37.5-mg kit: (NDC 72526-103-11): A white to almost white powder provided in a vial with a purple flip-off cap (NDC 72526-203-01); a pre-filled syringe containing 2 mL of a colorless, clear diluent (NDC 72526-801-01); a needle; and a vial adapter.

RYKINDO 50-mg kit: (NDC 72526-104-11): A white to almost white powder provided in a vial with a blue flip-off cap (NDC 72526-204-01); a pre-filled syringe containing 2 mL of a colorless, clear diluent (NDC 72526-801-01); a needle; and a vial adapter.

Storage and Handling

Store kit in refrigerator at 2° to 8°C (36° to 46°F). Protect from light.

If refrigeration is unavailable, RYKINDO can be stored in its unopened original packaging at temperatures not exceeding 77°F (25°C) for no more than 7 days prior to administration.

After removal from the refrigerator, use RYKINDO within 7 days or discard.

17 PATIENT COUNSELING INFORMATION

Neuroleptic Malignant Syndrome (NMS)

Counsel patients about a potentially fatal adverse reaction, Neuroleptic Malignant Syndrome (NMS), that has been reported in association with administration of antipsychotic drugs. Advise patients, family members, or caregivers to contact the healthcare provider or report to the emergency room if they experience signs and symptoms of NMS [see Warnings and Precautions (5.3)].

Tardive Dyskinesia

Counsel patients on the signs and symptoms of tardive dyskinesia and to contact their healthcare provider if these abnormal movements occur [see Warnings and Precautions (5.4)].

Metabolic Changes

Educate patients about the risk of metabolic changes, how to recognize symptoms of hyperglycemia and diabetes mellitus and the need for specific monitoring, including blood glucose, lipids, and weight [see Warnings and Precautions (5.5)].

Hyperprolactinemia

Counsel patients on signs and symptoms of hyperprolactinemia that may be associated with chronic use of RYKINDO. Advise them to seek medical attention if they experience any of the following: amenorrhea or galactorrhea in females, erectile dysfunction or gynecomastia in males [see Warnings and Precautions (5.6)].

Orthostatic Hypotension and Syncope

Educate patients about the risk of orthostatic hypotension and syncope, particularly at the time of initiating treatment, re-initiating treatment, or increasing the dose [see Warnings and Precautions (5.7)].

Leukopenia/Neutropenia

Advise patients with a pre-existing low WBC or a history of drug induced leukopenia/neutropenia that they should have their CBC monitored while being treated with RYKINDO [see Warnings and Precautions (5.9)].

Potential for Cognitive and Motor Impairment

Inform patients that RYKINDO has the potential to impair judgment, thinking, or motor skills. Caution patients about performing activities requiring mental alertness, such as operating hazardous machinery or operating a motor vehicle, until they are reasonably certain that treatment with RYKINDO does not affect them adversely [see Warnings and Precautions (5.10)].

Priapism

Advise patients of the possibility of painful or prolonged penile erections (priapism). Instruct the patient to seek immediate medical attention in the event of priapism [see Warnings and Precautions (5.13)].

Heat Exposure and Dehydration

Educate patients regarding appropriate care in avoiding overheating and dehydration [see Warnings and Precautions (5.14)].

Concomitant Medication

Advise patients to inform their healthcare providers if they are taking, or plan to take, any prescription or over-the-counter drugs, since there is a potential for interactions [see Drug Interactions (7)].

Alcohol

Advise patients to avoid alcohol during treatment with RYKINDO [see Drug Interactions (7.1)].

Pregnancy

Advise patients to notify their healthcare provider if they become pregnant or intend to become pregnant during treatment with RYKINDO. Advise patients that RYKINDO may cause extrapyramidal and/or withdrawal symptoms (agitation, hypertonia, hypotonia, tremor, somnolence, respiratory distress, and feeding disorder) in a neonate. Advise patients that there is a pregnancy registry that monitors pregnancy outcomes in women exposed to RYKINDO during pregnancy [see Use in Specific Populations (8.1)].

Lactation

Advise breastfeeding women using RYKINDO to monitor infants for somnolence, failure to thrive, jitteriness, and EPS (tremors and abnormal muscle movements) and to seek medical care if they notice these signs [see Use in Specific Populations (8.2)].

Infertility

Advise females of reproductive potential that RYKINDO may impair fertility due to an increase in serum prolactin levels. The effects on fertility are reversible [see Use in Specific Populations (8.3)].

RYKINDO is manufactured by:
Shandong Luye Pharmaceutical Co., Ltd.
Yantai, Shandong Province, China

INSTRUCTIONS FOR USE

RYKINDO® [ray-KIN-do]
(risperidone)
injection, for gluteal intramuscular use

This Instruction for Use contains information on how to inject RYKINDO®

Important Information You Need to Know Before Injecting RYKINDO®

• For gluteal intramuscular injection use only

For gluteal intramuscular injection only. Do not inject by any other route. Alternate injections between the two buttocks.

• Wait 30 minutes

Remove dose pack from the refrigerator and allow to sit at room temperature for at least 30 minutes prior to preparation. Do not warm any other way. Prepare medication when you are ready to administer the dose.

• Use components provided

The components in this dose pack are specifically designed for use with RYKINDO. RYKINDO must be reconstituted only in the diluent supplied in the dose pack. Do not substitute ANY components of the dose pack.

• Do not store suspension after reconstitution.

Administer dose as soon as possible after reconstitution to avoid settling.

• Proper dosing

The entire contents of the vial must be administered to ensure the intended dose of RYKINDO is delivered.

• Do not reuse.

RYKINDO® is for one-time use only. Do not reuse RYKINDO.

The components of the single-dose kit are shown in Figure 1.

Figure1: Single-dose Kit Components

Preparing to Inject RYKINDO®

Step 1. Take out kit and connect vial adapter to vial

Wait 30 minutes
Remove dose pack from the refrigerator and allow to sit at room temperature for at least 30 minutes before reconstituting.
Do not warm any other way.

Remove cap from vial
Flip off colored cap from vial.
Wipe top of the gray stopper with an alcohol swab. Allow to air dry.
Do not remove gray rubber stopper.

Prepare vial adapter
Hold sterile blister as shown. Peel back and remove paper backing.
Do not remove vial adapter from blister.
Do not touch spike tip at any time. This will result in contamination.

Connect vial adapter to vial
Place vial on a hard surface and hold by the base. Center vial adapter over the gray rubber stopper. Push vial adapter straight down onto vial top until it snaps securely into place.
Do not place vial adapter on at an angle or diluent may leak upon transfer to the vial.

Step 2. Connect prefilled syringe to vial adapter

Remove sterile blister

Keep vial vertical to prevent leakage. Hold base of vial and pull up on the sterile blister to remove.
Do not shake.
Do not touch exposed luer opening on vial adapter.
This will result in contamination.

Use proper grip
Hold by the LUER-LOK ADAPTER at the tip of the syringe.
Do not hold syringe by the glass barrel during assembly.

Remove cap
Holding the transparent LUER-LOK ADAPTER, unscrew the translucent gray cap.
Do not snap or cut off the translucent gray cap.
Do not touch syringe tip. This will result in contamination.

The unscrewed cap can be discarded.

Connect syringe to vial adapter
Hold vial adapter by skirt to keep stationary.
Hold syringe by the LUER-LOK ADAPTER then turn it to connect with the luer opening of the vial adapter.
Do not hold the glass syringe barrel. This may cause the LUER-LOK ADAPTER to loosen or detach.
Attach the syringe to the vial adapter with a firm clockwise twisting motion until it feels snug.
Do not over-tighten. Over-tightening may cause the syringe tip to break.

Step 3. Reconstitute powder

Inject diluent
Inject entire amount of diluent from syringe into the vial.

Suspend powder in diluent
Continuing to hold down the plunger rod, shake vigorously for at least 30 seconds, as shown.
Check the suspension. When properly mixed, the suspension appears uniform, thick and milky in color.
Immediately proceed to the next step so suspension does not settle.

Transfer suspension to syringe
Invert vial completely. Slowly pull plunger rod down to withdraw entire contents from the vial into the syringe.

Remove vial adapter
Hold the LUER-LOK ADAPTER on the syringe and unscrew from vial adapter.
Tear section of the vial label at the perforation. Apply detached label to the syringe for identification purposes.
Discard both vial and vial adapter appropriately.

Step 4. Attach needle

Take out needle
Take out needle for gluteal injection.

Attach needle
Peel blister pouch open part way and use to grasp the base of the needle, as shown.
Holding the LUER-LOK ADAPTER on the syringe, attach syringe to needle luer connection with a firm clockwise twisting motion until snug.
Do not touch needle luer opening. This will result in contamination.

Resuspend powder
Fully remove the blister pouch.
Just before injection, shake syringe vigorously for 20 to 30 seconds until there is no deposition of powder, as some settling will have occurred.

Step 5. Inject RYKINDO®

Remove transparent needle protector
Move the needle safety device back towards the syringe, as shown. Then hold the LUER-LOK ADAPTER on syringe and carefully pull the transparent needle protector straight off.
Do not twist transparent needle protector, as the luer connection may loosen.

Remove air bubbles
Hold syringe upright and tap gently to make any air bubbles rise to the top.
Slowly and carefully press plunger rod upward to remove air.

Inject
Immediately inject entire contents of syringe intramuscularly into the upper outer quadrant of the gluteal muscle of the patient. Do not administer by any other route.

Secure needle in safety device
Using one hand, place needle safety device at a 45-degree angle on a hard, flat surface. Press down with a firm, quick motion until needle is fully engaged in safety device.
Avoid needle stick injury:
Do not use two hands.
Do not intentionally disengage or mishandle the needle safety device.
Do not attempt to straighten the needle or engage the safety device if the needle is bent or damaged.

Properly dispose of syringes
Check to confirm needle safety device is fully engaged.
Discard in an approved sharps container.

Storing RYKINDO®

Store kit in refrigerator at 2° to 8°C (36° to 46°F). Protect from light.

If refrigeration is unavailable, RYKINDO can be stored in its unopened original packaging at temperatures not exceeding 77°F (25°C) for no more than 7 days prior to administration. After removal from the refrigerator, use RYKINDO within 7 days or discard.

For product or service related questions, call 1-800-548-9765 or visit www.rykindo.com.

Shandong Luye Pharmaceutical Co., Ltd.
No.15 Chuangye Road, High-tech Zone,
Yantai, Shandong, 264003
China

This Instruction for Use has been approved by the U.S. Food and Drug Administration.
Issued: 05/2023

PRINCIPAL DISPLAY PANEL - 25 mg Kit Carton

25 mg
Kit

Rykindo®
(risperiDONE) for extended-release
injectable suspension

KIT CONTENTS:

- One 25 mg vial of risperiDONE for extended-release injectable suspension
- One pre-filled syringe containing 2 mL of diluent
- One Vial Adapter
- One 20-gauge 2-inch safety needle for gluteal intramuscular injection only

Do not substitute any components of the kit.

For gluteal intramuscular injection only.
Each injection should be administered by a healthcare professional.

Rx only
Single dose

Store Kit in Refrigerator
(see bottom panel for storage conditions)

PLEASE READ COMPLETE
INSTRUCTIONS PRIOR TO USE.

NDC 72526-102-11

PRINCIPAL DISPLAY PANEL - 37.5 mg Kit Carton

37.5 mg
Kit

Rykindo®
(risperiDONE) for extended-release
injectable suspension

KIT CONTENTS:

- One 37.5 mg vial of risperiDONE for extended-release injectable suspension
- One pre-filled syringe containing 2 mL of diluent
- One Vial Adapter
- One 20-gauge 2-inch safety needle for gluteal intramuscular injection only

Do not substitute any components of the kit.

For gluteal intramuscular injection only.
Each injection should be administered by a healthcare professional.

Rx only
Single dose

Store Kit in Refrigerator
(see bottom panel for storage conditions)

PLEASE READ COMPLETE
INSTRUCTIONS PRIOR TO USE.

NDC 72526-103-11

PRINCIPAL DISPLAY PANEL - 50 mg Kit Carton

50 mg
Kit

Rykindo®
(risperiDONE) for extended-release
injectable suspension

KIT CONTENTS:

- One 50 mg vial of risperiDONE for extended-release injectable suspension
- One pre-filled syringe containing 2 mL of diluent
- One Vial Adapter
- One 20-gauge 2-inch safety needle for gluteal intramuscular injection only

Do not substitute any components of the kit.

For gluteal intramuscular injection only.
Each injection should be administered by a healthcare professional.

Rx only
Single dose

Store Kit in Refrigerator
(see bottom panel for storage conditions)

PLEASE READ COMPLETE
INSTRUCTIONS PRIOR TO USE.

NDC 72526-104-11